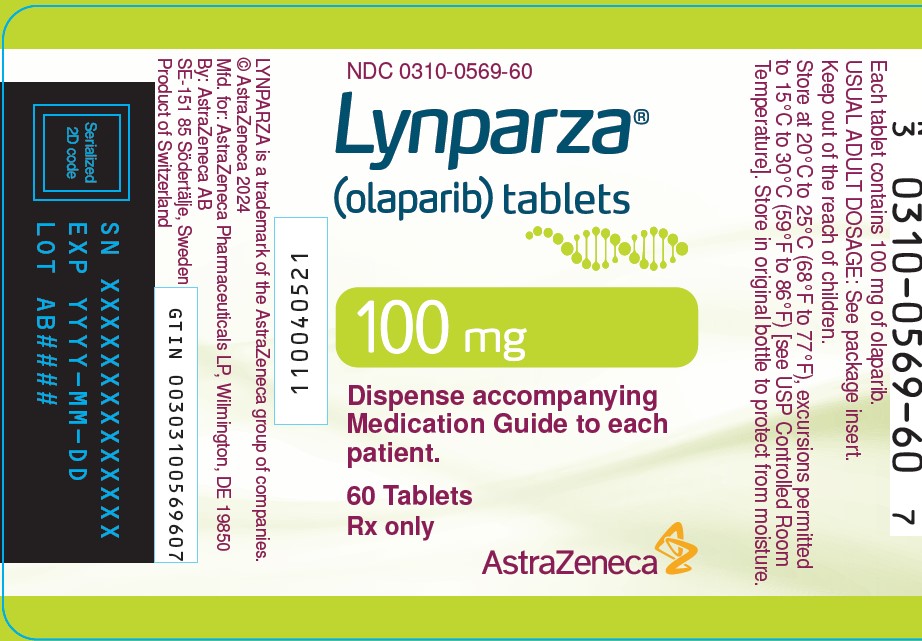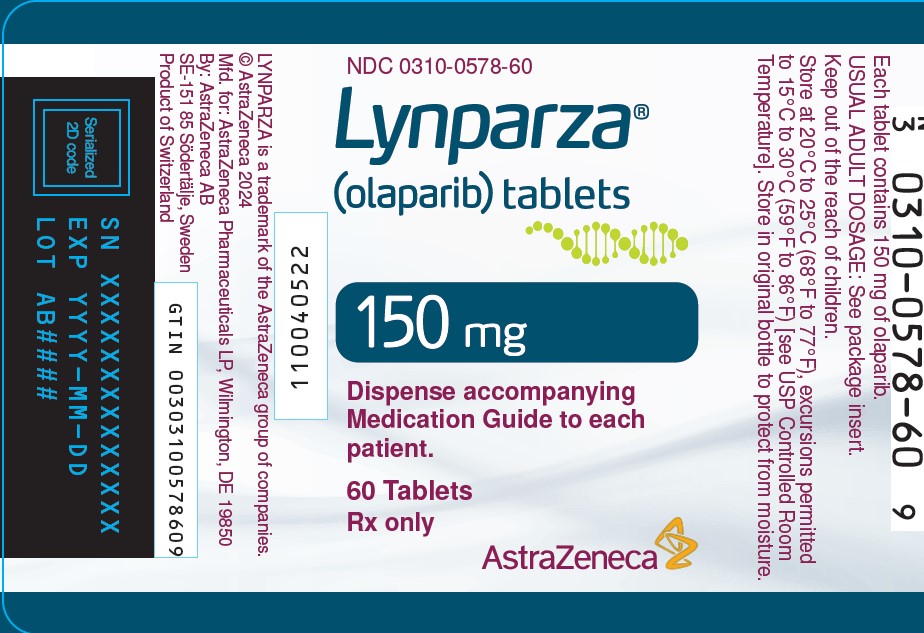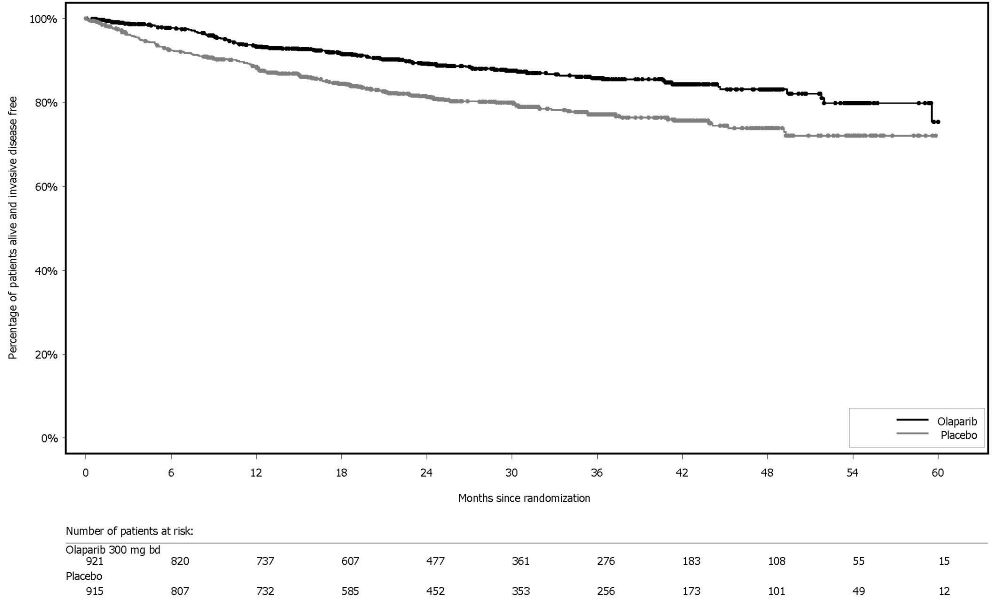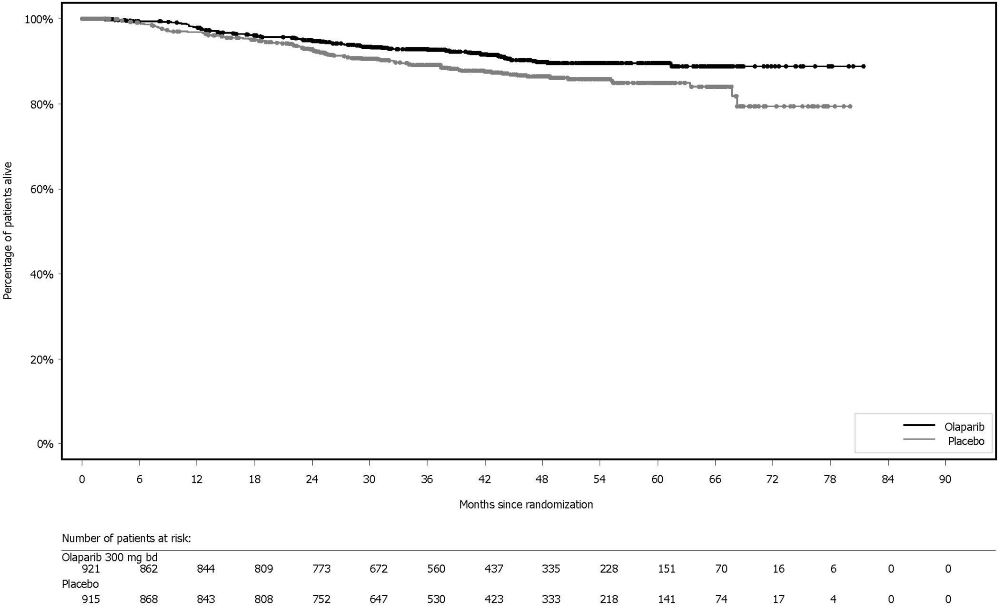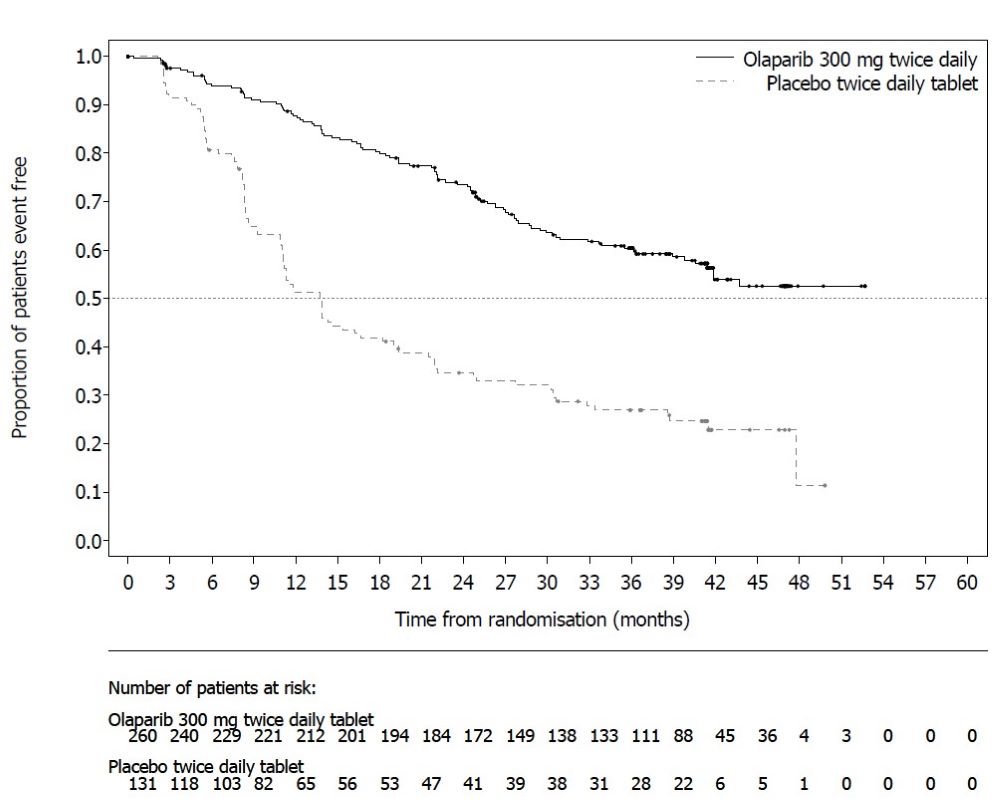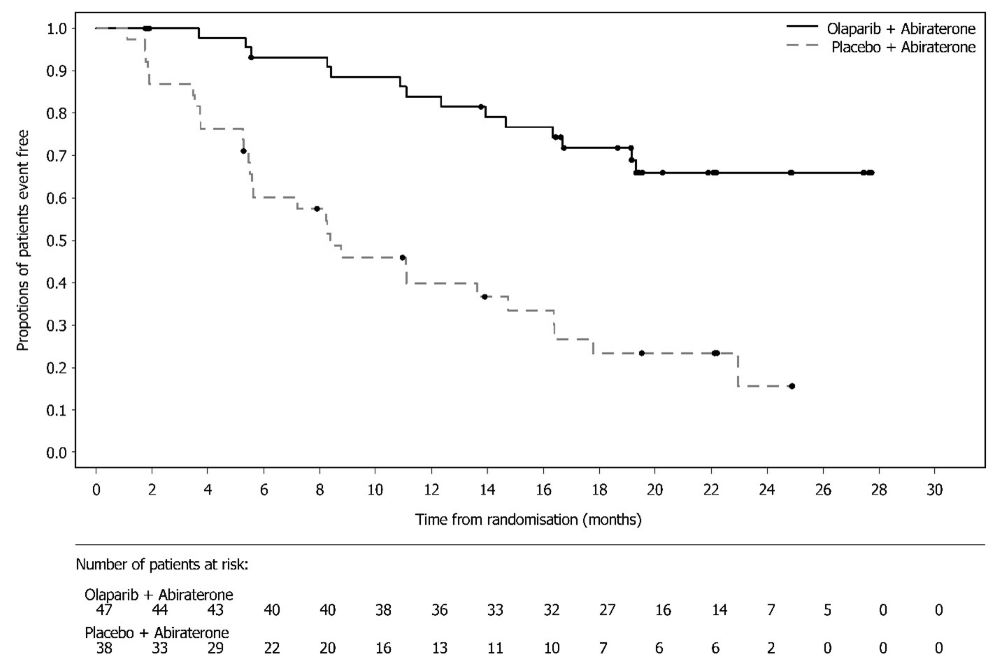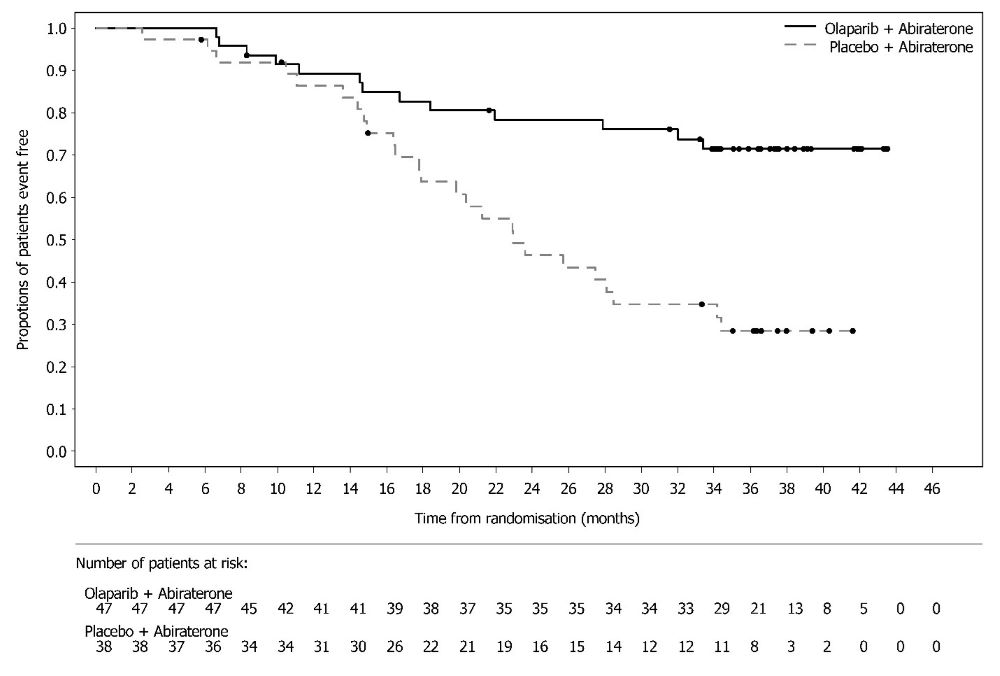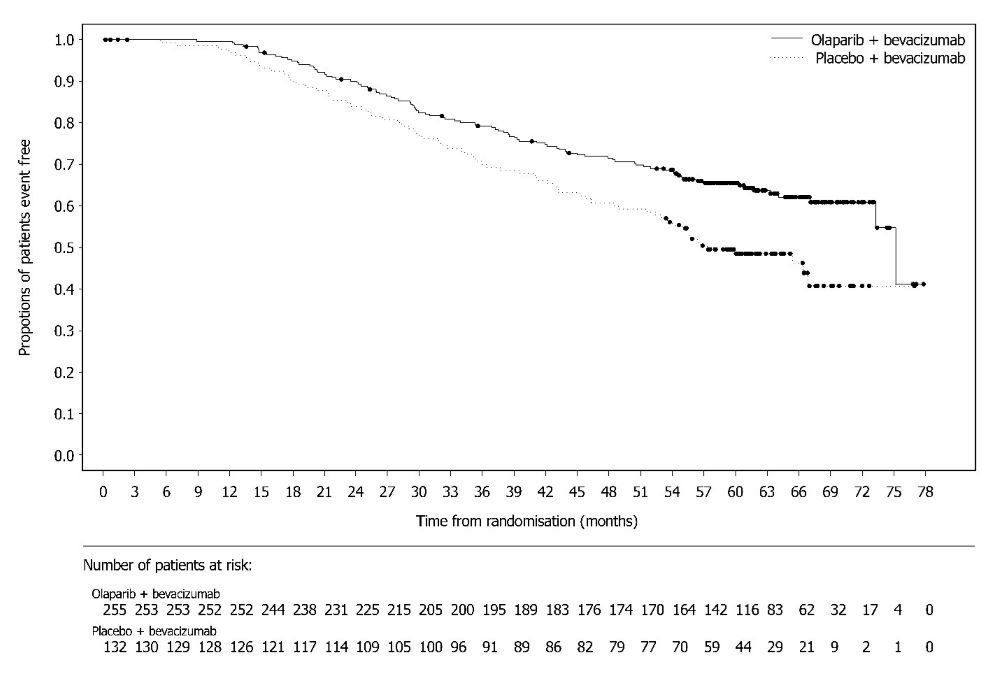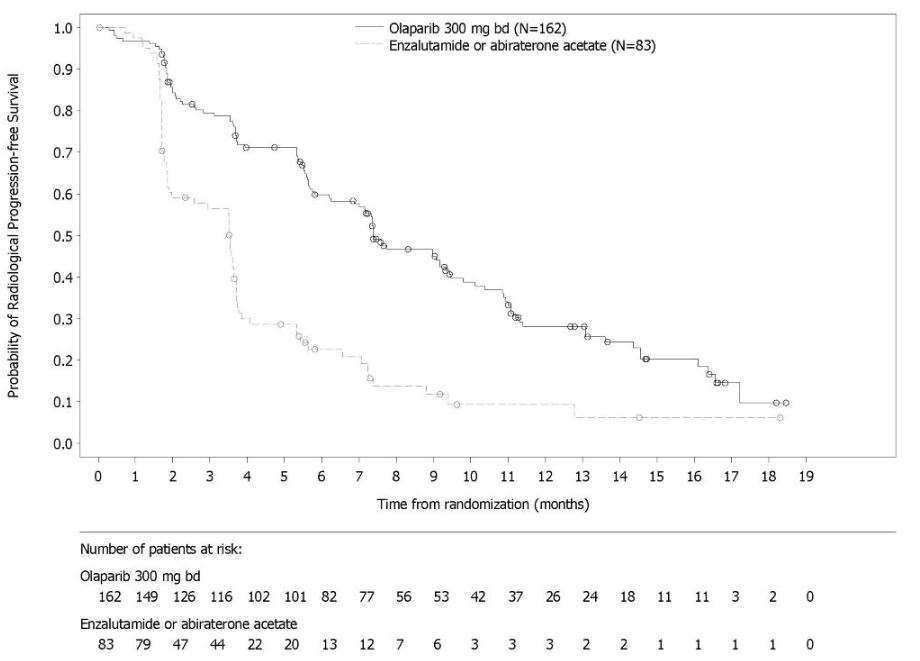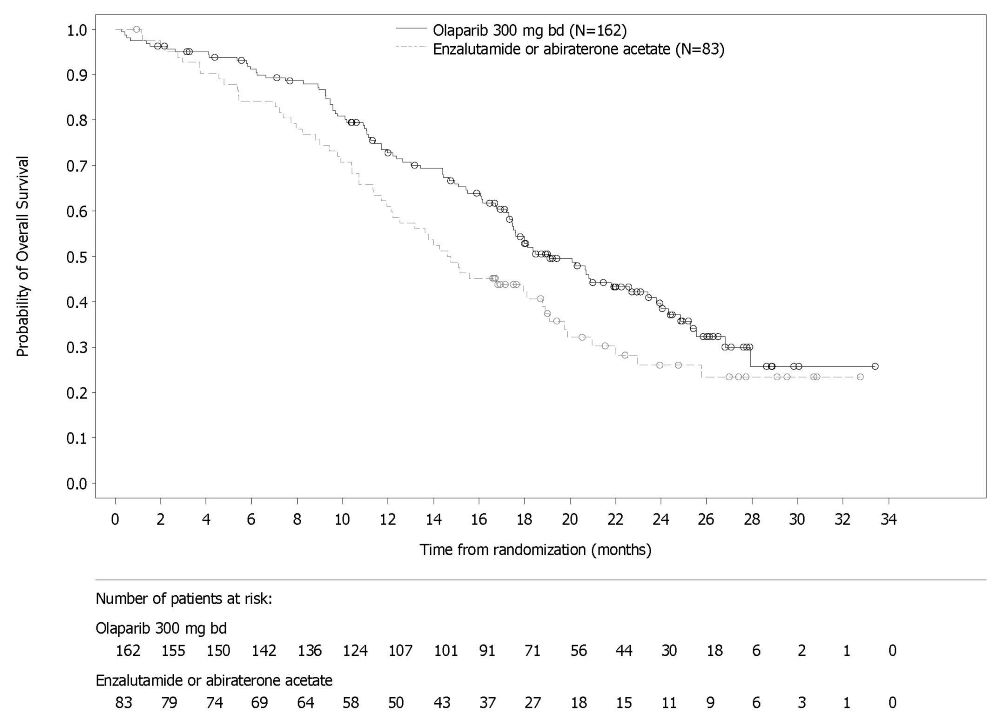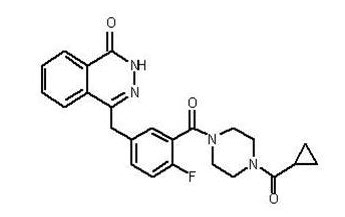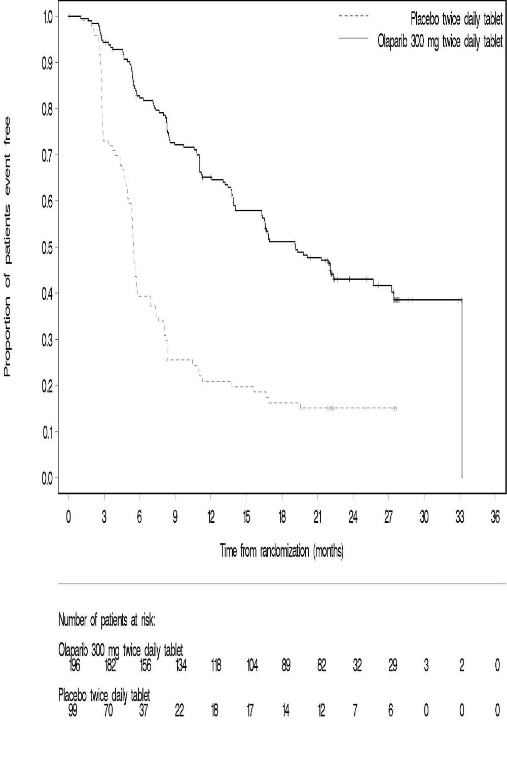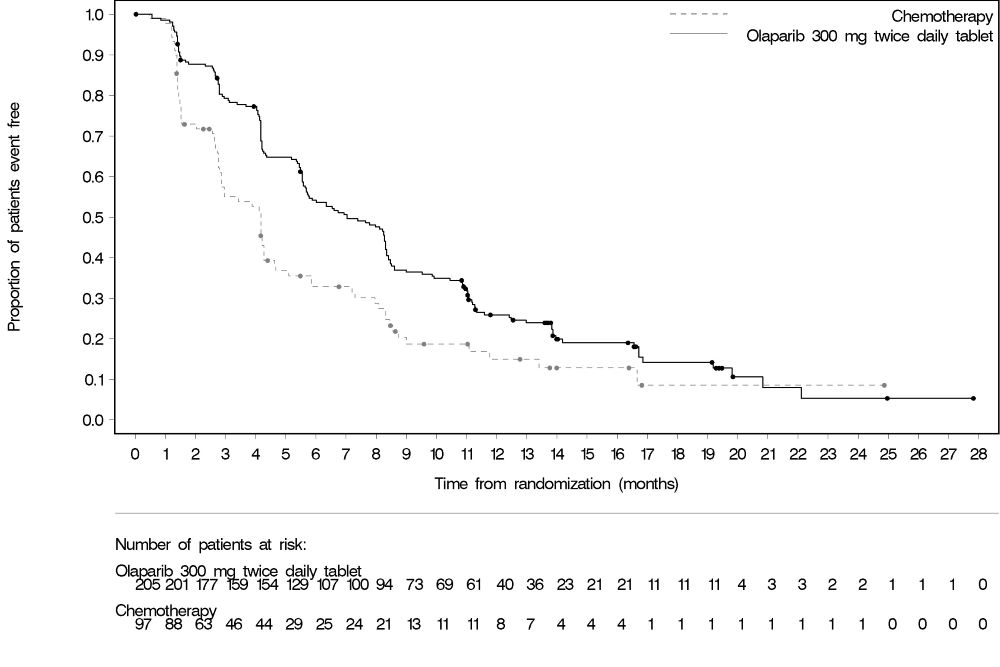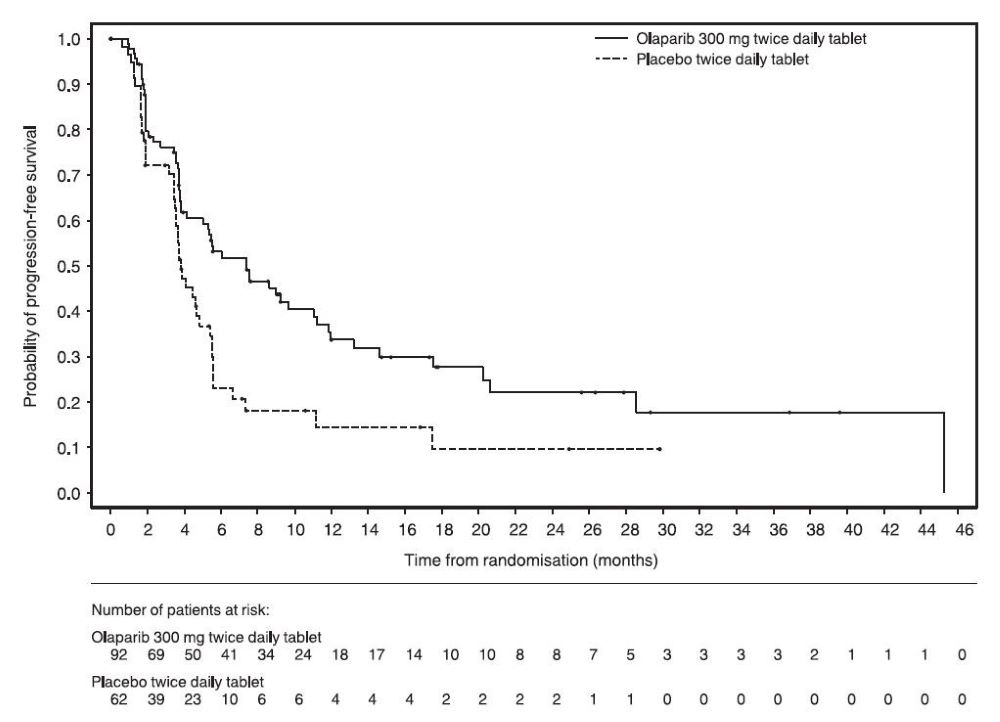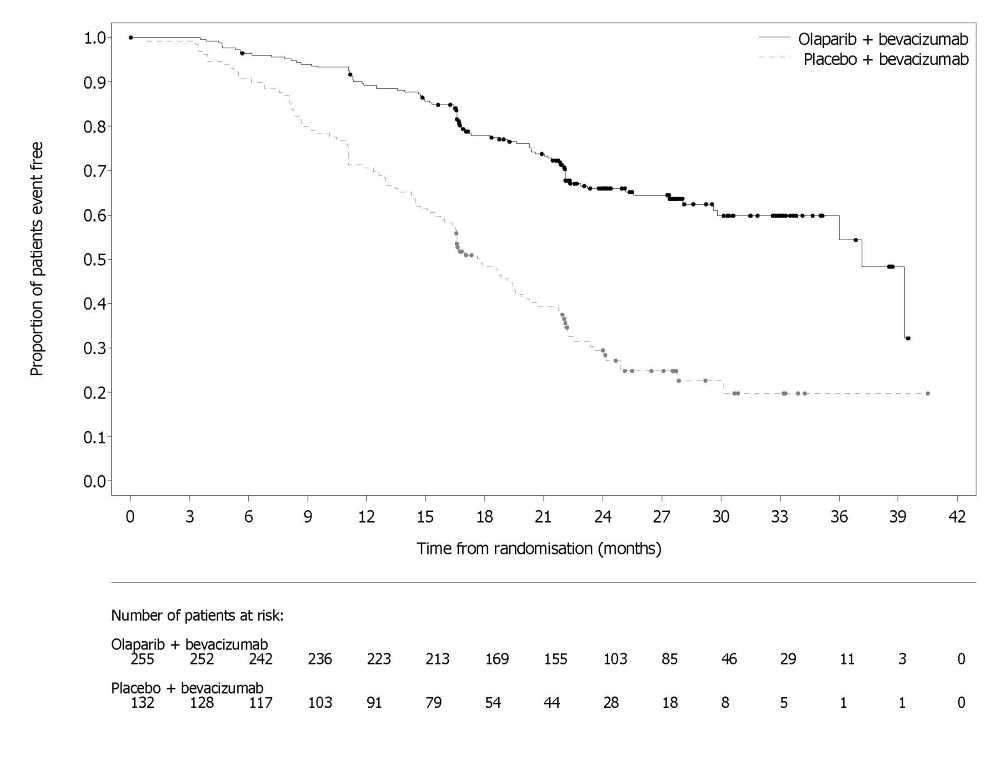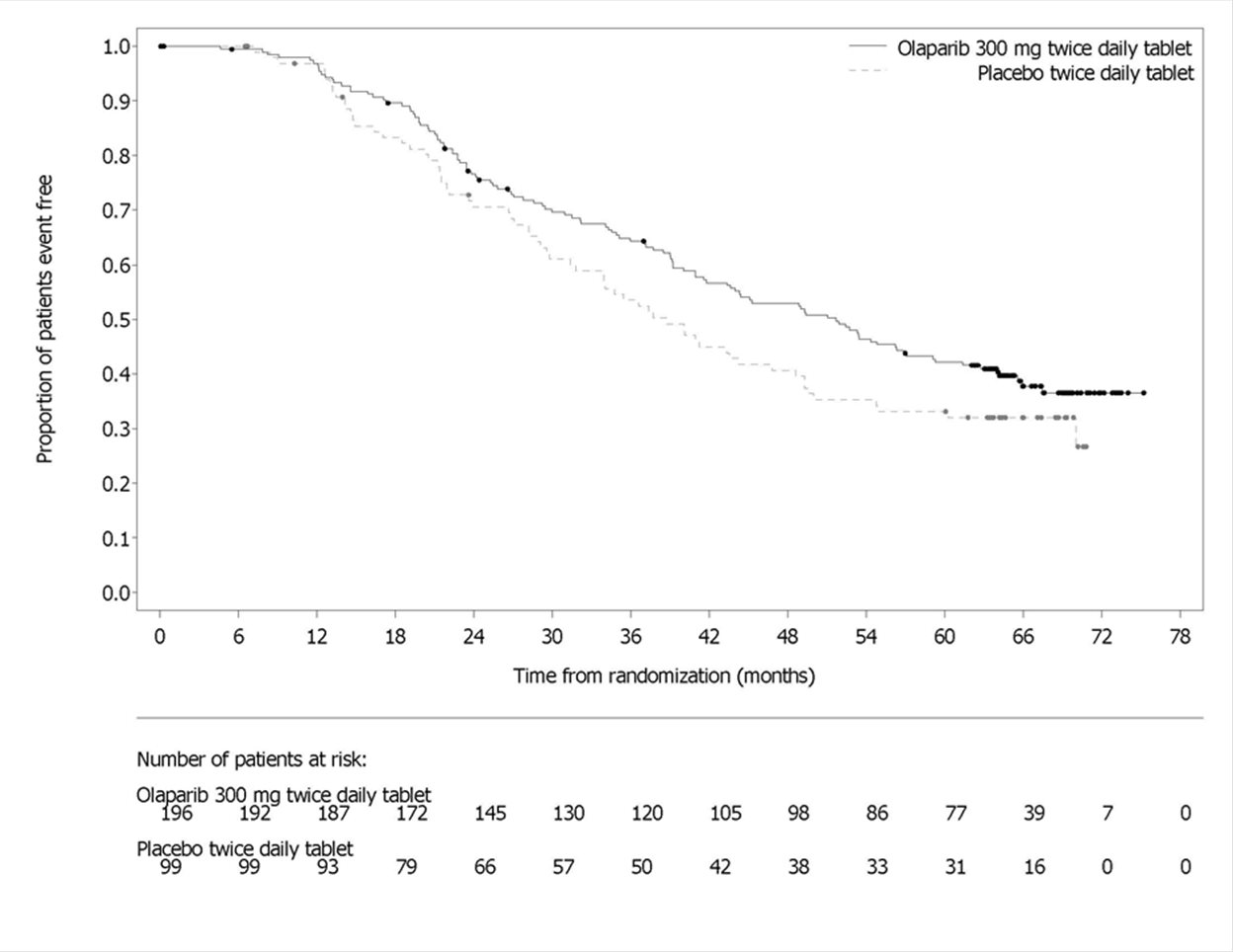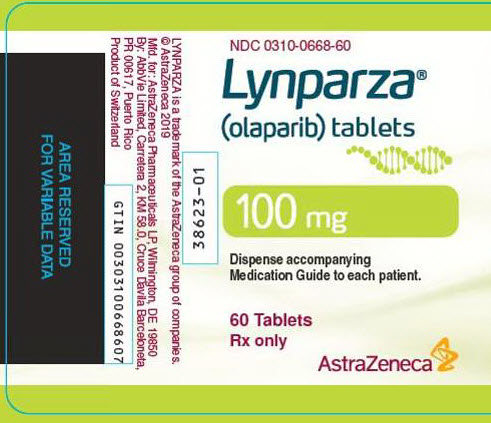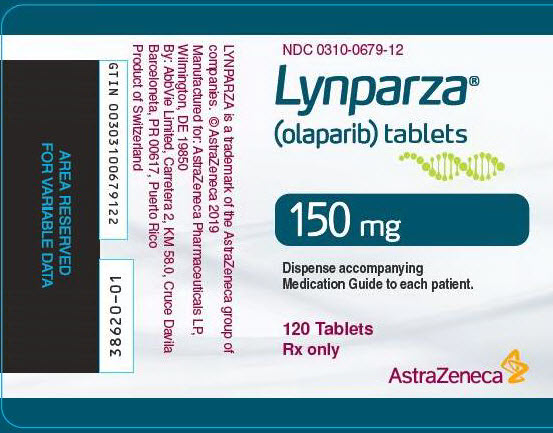 DRUG LABEL: Lynparza
NDC: 0310-0668 | Form: TABLET, FILM COATED
Manufacturer: AstraZeneca Pharmaceuticals LP
Category: prescription | Type: HUMAN PRESCRIPTION DRUG LABEL
Date: 20250710

ACTIVE INGREDIENTS: OLAPARIB 100 mg/1 1
INACTIVE INGREDIENTS: COPOVIDONE K25-31; FERRIC OXIDE YELLOW; FERROSOFERRIC OXIDE; HYPROMELLOSE, UNSPECIFIED; MANNITOL; POLYETHYLENE GLYCOL 400; SILICON DIOXIDE; SODIUM STEARYL FUMARATE; TITANIUM DIOXIDE; WATER

HIGHLIGHTS OF PRESCRIBING INFORMATION

These highlights do not include all the information needed to use LYNPARZA safely and effectively. See full prescribing information for LYNPARZA.
LYNPARZA® (olaparib) tablets, for oral use
Initial U.S. Approval: 2014

RECENT MAJOR CHANGES

Warnings and Precautions (5.2, 5.4) 7/2025

1 INDICATIONS AND USAGE

Lynparza is a poly (ADP-ribose) polymerase (PARP) inhibitor indicated:

Ovarian cancer

- for the maintenance treatment of adult patients with deleterious or suspected deleterious germline or somatic BRCA-mutated advanced epithelial ovarian, fallopian tube or primary peritoneal cancer who are in complete or partial response to first-line platinum-based chemotherapy. Select patients for therapy based on an FDA-approved companion diagnostic for Lynparza. (1.1, 2.1)
- in combination with bevacizumab for the maintenance treatment of adult patients with advanced epithelial ovarian, fallopian tube or primary peritoneal cancer who are in complete or partial response to first-line platinum-based chemotherapy and whose cancer is associated with homologous recombination deficiency (HRD)-positive status defined by either:
  - a deleterious or suspected deleterious BRCA mutation, and/or
  - genomic instability.
Select patients for therapy based on an FDA-approved companion diagnostic for Lynparza. (1.2, 2.1)
- for the maintenance treatment of adult patients with deleterious or suspected deleterious germline or somatic BRCA-mutated recurrent epithelial ovarian, fallopian tube or primary peritoneal cancer, who are in complete or partial response to platinum-based chemotherapy. Select patients for therapy based on an FDA-approved companion diagnostic for Lynparza. (1.3, 2.1)

Breast cancer

- for the adjuvant treatment of adult patients with deleterious or suspected deleterious gBRCAm human epidermal growth factor receptor 2 (HER2)-negative high risk early breast cancer who have been treated with neoadjuvant or adjuvant chemotherapy. Select patients for therapy based on an FDA-approved companion diagnostic for Lynparza. (1.4, 2.1)
- for the treatment of adult patients with deleterious or suspected deleterious gBRCAm, HER2-negative metastatic breast cancer who have been treated with chemotherapy in the neoadjuvant, adjuvant or metastatic setting. Patients with hormone receptor (HR)-positive breast cancer should have been treated with a prior endocrine therapy or be considered inappropriate for endocrine therapy. Select patients for therapy based on an FDA-approved companion diagnostic for Lynparza. (1.5, 2.1)

Pancreatic cancer

- for the maintenance treatment of adult patients with deleterious or suspected deleterious gBRCAm metastatic pancreatic adenocarcinoma whose disease has not progressed on at least 16 weeks of a first-line platinum-based chemotherapy regimen. Select patients for therapy based on an FDA-approved companion diagnostic for Lynparza. (1.6, 2.1)

Prostate cancer

- for the treatment of adult patients with deleterious or suspected deleterious germline or somatic homologous recombination repair (HRR) gene-mutated metastatic castration-resistant prostate cancer (mCRPC) who have progressed following prior treatment with enzalutamide or abiraterone. Select patients for therapy based on an FDA-approved companion diagnostic for Lynparza. (1.7, 2.1)
- in combination with abiraterone and prednisone or prednisolone for the treatment of adult patients with deleterious or suspected deleterious BRCA-mutated (BRCAm) metastatic castration-resistant prostate cancer (mCRPC). Select patients for therapy based on an FDA-approved companion diagnostic for Lynparza. (1.8, 2.1)

2 DOSAGE AND ADMINISTRATION

- Recommended dosage is 300 mg taken orally twice daily with or without food. See Full Prescribing Information for the recommended duration. (2.2)
- Patients receiving Lynparza for mCRPC should also receive a gonadotropin-releasing hormone (GnRH) analog concurrently or should have had bilateral orchiectomy. (2.2)
- For moderate renal impairment (CLcr 31-50 mL/min), reduce Lynparza dosage to 200 mg orally twice daily. (2.5)

3 DOSAGE FORMS AND STRENGTHS

Tablets: 150 mg, 100 mg (3)

4 CONTRAINDICATIONS

None. (4)

5 WARNINGS AND PRECAUTIONS

- Myelodysplastic Syndrome/Acute Myeloid Leukemia (MDS/AML): Occurred in approximately 1.2% of patients with various BRCAm, gBRCAm, HRR gene-mutated or HRD-positive cancers exposed to Lynparza and the majority of events had a fatal outcome. Monitor patients for hematological toxicity at baseline and monthly thereafter. Discontinue if MDS/AML is confirmed. (5.1)
- Pneumonitis: Occurred in 1.0% of patients exposed to Lynparza, and some cases were fatal. Interrupt treatment if pneumonitis is suspected. Discontinue if pneumonitis is confirmed. (5.2)
- Venous thromboembolism (VTE), including severe or fatal pulmonary embolism (PE), occurred in patients treated with Lynparza. VTE occurred in 8% of patients with mCRPC. Monitor patients for signs and symptoms of VTE and PE and treat as medically appropriate. (5.3)
- Hepatotoxicity, Including Drug-induced liver injury (DILI): Occurred in patients treated with Lynparza. If DILI is suspected, interrupt Lynparza. If DILI is confirmed, discontinue treatment. (5.4)
- Embryo-Fetal Toxicity: Can cause fetal harm. Advise of the potential risk to a fetus and to use effective contraception. (5.5, 8.1, 8.3)

6 ADVERSE REACTIONS

Most common adverse reactions (≥10%):

- as a single agent were nausea, fatigue (including asthenia), anemia, vomiting, diarrhea, decreased appetite, headache, dysgeusia, cough, neutropenia, dyspnea, dizziness, dyspepsia, leukopenia, and thrombocytopenia. (6.1)
- in combination with bevacizumab were nausea, fatigue (including asthenia), anemia, lymphopenia, vomiting, diarrhea, neutropenia, leukopenia, urinary tract infection, and headache. (6.1)
- in combination with abiraterone and prednisone or prednisolone were anemia, fatigue, nausea, diarrhea, decreased appetite, lymphopenia, dizziness, and abdominal pain. (6.1)

To report SUSPECTED ADVERSE REACTIONS, contact AstraZeneca at 1-800-236-9933 or FDA at 1-800-FDA-1088 or www.fda.gov/medwatch.

7 DRUG INTERACTIONS

- Strong or moderate CYP3A inhibitors: Avoid concomitant use. If concomitant use cannot be avoided, reduce Lynparza dosage. (2.4, 7.2, 12.3)
- Strong or moderate CYP3A inducers: Avoid concomitant use. (7.2, 12.3)

8 USE IN SPECIFIC POPULATIONS

Lactation: Advise women not to breastfeed. (8.2)

FULL PRESCRIBING INFORMATION

1 INDICATIONS AND USAGE

1.1 First-Line Maintenance Treatment of BRCA-mutated Advanced Ovarian Cancer

Lynparza is indicated for the maintenance treatment of adult patients with deleterious or suspected deleterious germline or somatic BRCA-mutated advanced epithelial ovarian, fallopian tube or primary peritoneal cancer who are in complete or partial response to first-line platinum-based chemotherapy. Select patients for therapy based on an FDA-approved companion diagnostic for Lynparza [see Dosage and Administration (2.1)].

1.2 First-line Maintenance Treatment of HRD-positive Advanced Ovarian Cancer in Combination with Bevacizumab

Lynparza is indicated in combination with bevacizumab for the maintenance treatment of adult patients with advanced epithelial ovarian, fallopian tube or primary peritoneal cancer who are in complete or partial response to first-line platinum-based chemotherapy and whose cancer is associated with homologous recombination deficiency (HRD)-positive status defined by either:

  - a deleterious or suspected deleterious BRCA mutation, and/or
  - genomic instability.

Select patients for therapy based on an FDA-approved companion diagnostic for Lynparza [see Dosage and Administration (2.1)].

1.3 Maintenance Treatment of BRCA-mutated Recurrent Ovarian Cancer

Lynparza is indicated for the maintenance treatment of adult patients with deleterious or suspected deleterious germline or somatic BRCA-mutated recurrent epithelial ovarian, fallopian tube or primary peritoneal cancer, who are in complete or partial response to platinum-based chemotherapy. Select patients for therapy based on an FDA-approved companion diagnostic for Lynparza [see Dosage and Administration (2.1)].

1.4 Adjuvant Treatment of Germline BRCA-mutated HER2-negative High Risk Early Breast Cancer

Lynparza is indicated for the adjuvant treatment of adult patients with deleterious or suspected deleterious gBRCAm human epidermal growth factor receptor 2 (HER2)-negative high risk early breast cancer who have been treated with neoadjuvant or adjuvant chemotherapy. Select patients for therapy based on an FDA-approved companion diagnostic for Lynparza [see Dosage and Administration (2.1)].

1.5 Germline BRCA-mutated HER2-negative Metastatic Breast Cancer

Lynparza is indicated for the treatment of adult patients with deleterious or suspected deleterious gBRCAm, HER2-negative metastatic breast cancer, who have been treated with chemotherapy in the neoadjuvant, adjuvant, or metastatic setting. Patients with hormone receptor (HR)-positive breast cancer should have been treated with a prior endocrine therapy or be considered inappropriate for endocrine therapy. Select patients for therapy based on an FDA-approved companion diagnostic for Lynparza [see Dosage and Administration (2.1)].

1.6 First-Line Maintenance Treatment of Germline BRCA-mutated Metastatic Pancreatic Adenocarcinoma

Lynparza is indicated for the maintenance treatment of adult patients with deleterious or suspected deleterious gBRCAm metastatic pancreatic adenocarcinoma whose disease has not progressed on at least 16 weeks of a first-line platinum-based chemotherapy regimen. Select patients for therapy based on an FDA-approved companion diagnostic for Lynparza [see Dosage and Administration (2.1)].

1.7 HRR Gene-mutated Metastatic Castration-Resistant Prostate Cancer

Lynparza is indicated for the treatment of adult patients with deleterious or suspected deleterious germline or somatic homologous recombination repair (HRR) gene-mutated metastatic castration-resistant prostate cancer (mCRPC) who have progressed following prior treatment with enzalutamide or abiraterone. Select patients for therapy based on an FDA-approved companion diagnostic for Lynparza [see Dosage and Administration (2.1)].

1.8 Treatment of BRCA-mutated Metastatic Castration-Resistant Prostate Cancer in Combination with Abiraterone and Prednisone or Prednisolone

Lynparza is indicated in combination with abiraterone and prednisone or prednisolone for the treatment of adult patients with deleterious or suspected deleterious BRCA-mutated (BRCAm) metastatic castration-resistant prostate cancer (mCRPC). Select patients for therapy based on an FDA-approved companion diagnostic for Lynparza [see Dosage and Administration (2.1)].

2 DOSAGE AND ADMINISTRATION

2.1 Patient Selection

Information on FDA-approved tests for the detection of genetic mutations is available at http://www.fda.gov/companiondiagnostics.

Select patients for treatment with Lynparza based on the presence of deleterious or suspected deleterious HRR gene mutations, including BRCA mutations, or genomic instability based on the indication, biomarker, and sample type (Table 1).

Table 1 Biomarker Testing for Patient Selection [Where testing fails or tissue sample is unavailable/insufficient, or when germline testing is negative, consider using an alternative test, if available.]
Indication | Biomarker | Sample type
Indication | Biomarker | Tumor | Blood | Plasma; (ctDNA)
First-line maintenance treatment of germline or somatic BRCAm advanced ovarian cancer | BRCA1m, BRCA2m | X | X
First-line maintenance treatment of HRD-positive advanced ovarian cancer in combination with bevacizumab | BRCA1m, BRCA2m and/or genomic instability | X
Maintenance treatment of germline or somatic BRCAm recurrent ovarian cancer | BRCA1m, BRCA2m | X | X
Adjuvant treatment of gBRCAm HER2-negative high risk early breast cancer | gBRCA1m, gBRCA2m |  | X
gBRCAm HER2-negative metastatic breast cancer | gBRCA1m, gBRCA2m |  | X
First-line maintenance treatment of germline BRCA-mutated metastatic pancreatic adenocarcinoma | gBRCA1m, gBRCA2m |  | X
Germline or somatic HRR gene-mutated metastatic castration-resistant prostate cancer | ATMm, BRCA1m, BRCA2m, BARD1m, BRIP1m, CDK12m, CHEK1m, CHEK2m, FANCLm, PALB2m, RAD51Bm, RAD51Cm, RAD51Dm, RAD54Lm | X
Germline or somatic HRR gene-mutated metastatic castration-resistant prostate cancer | gBRCA1m, gBRCA2m |  | X
Germline or somatic HRR gene-mutated metastatic castration-resistant prostate cancer | ATMm, BRCA1m, BRCA2m |  |  | X
BRCA-mutated metastatic castration-resistant prostate cancer in combination with abiraterone and prednisone or prednisolone | BRCA1m, BRCA2m | X | X | X

2.2 Recommended Dosage

The recommended dosage of Lynparza is 300 mg taken orally twice daily, with or without food.

If a patient misses a dose of Lynparza, instruct patient to take their next dose at its scheduled time.

Instruct patients to swallow tablets whole. Do not chew, crush, dissolve, or divide tablet.

First-Line Maintenance Treatment of BRCA-mutated Advanced Ovarian Cancer

Continue treatment until disease progression, unacceptable toxicity, or completion of 2 years of treatment. Patients with a complete response (no radiological evidence of disease) at 2 years should stop treatment. Patients with evidence of disease at 2 years, who in the opinion of the treating healthcare provider can derive further benefit from continuous treatment, can be treated beyond 2 years.

First-Line Maintenance Treatment of HRD-positive Advanced Ovarian Cancer in Combination with Bevacizumab

Continue Lynparza treatment until disease progression, unacceptable toxicity, or completion of 2 years of treatment. Patients with a complete response (no radiological evidence of disease) at 2 years should stop treatment. Patients with evidence of disease at 2 years, who in the opinion of the treating healthcare provider can derive further benefit from continuous Lynparza treatment, can be treated beyond 2 years.

When used with Lynparza, the recommended dose of bevacizumab is 15 mg/kg every three weeks. Bevacizumab should be given for a total of 15 months including the period given with chemotherapy and given as maintenance. Refer to the Prescribing Information for bevacizumab when used in combination with Lynparza for more information.

Adjuvant Treatment of Germline BRCA-mutated HER2-negative High Risk Early Breast Cancer

Continue treatment for a total of 1 year, or until disease recurrence, or unacceptable toxicity, whichever occurs first. Patients receiving Lynparza for hormone receptor positive HER2-negative breast cancer should continue concurrent treatment with endocrine therapy as per current clinical practice guidelines.

Germline or Somatic BRCA-mutated Recurrent Ovarian Cancer, Germline BRCA-mutated HER2-negative Metastatic Breast Cancer, Germline BRCA-mutated Metastatic Pancreatic Adenocarcinoma, and HRR Gene-mutated Metastatic Castration-Resistant Prostate Cancer

Continue treatment until disease progression or unacceptable toxicity for:

  - Maintenance treatment of germline or somatic BRCA-mutated recurrent ovarian cancer.
  - Germline BRCA-mutated HER-2 negative metastatic breast cancer.
  - First-line maintenance treatment of germline BRCA-mutated metastatic pancreatic adenocarcinoma.
  - HRR gene-mutated metastatic castration-resistant prostate cancer.

BRCA-mutated Metastatic Castration-Resistant Prostate Cancer in Combination with Abiraterone and Prednisone or Prednisolone

Continue treatment until disease progression or unacceptable toxicity.

When used with Lynparza, the recommended dose of abiraterone is 1000 mg taken orally once daily. Abiraterone should be given in combination with prednisone or prednisolone 5 mg orally twice daily. Refer to the Prescribing Information for abiraterone for dosing information.

Patients with mCRPC should also receive a gonadotropin-releasing hormone (GnRH) analog concurrently or should have had bilateral orchiectomy.

2.3 Dosage Modifications for Adverse Reactions

To manage adverse reactions, consider interruption of treatment or dose reduction. The recommended dose reduction is 250 mg taken twice daily.

If a further dose reduction is required, then reduce to 200 mg taken twice daily.

2.4 Dosage Modifications for Concomitant Use with Strong or Moderate CYP3A Inhibitors

Avoid concomitant use of strong or moderate CYP3A inhibitors with Lynparza.

If concomitant use cannot be avoided, reduce Lynparza dosage to:

- 100 mg twice daily when used concomitantly with a strong CYP3A inhibitor.
- 150 mg twice daily when used concomitantly with a moderate CYP3A inhibitor.

After the inhibitor has been discontinued for 3 to 5 elimination half-lives, resume the Lynparza dose taken prior to initiating the CYP3A inhibitor [see Drug Interactions (7.2) and Clinical Pharmacology (12.3)].

2.5 Dosage Modifications for Renal Impairment

Moderate Renal Impairment

In patients with moderate renal impairment (CLcr 31-50 mL/min), reduce the Lynparza dosage to 200 mg orally twice daily [see Use in Specific Populations (8.6) and Clinical Pharmacology (12.3)].

3 DOSAGE FORMS AND STRENGTHS

Tablets:

- 150 mg: green to green/grey, oval, bi-convex, film-coated, with debossment ‘OP150’ on one side and plain on the reverse side.
- 100 mg: yellow to dark yellow, oval, bi-convex, film-coated, with debossment ‘OP100’ on one side and plain on the reverse side.

4 CONTRAINDICATIONS

None.

5 WARNINGS AND PRECAUTIONS

5.1 Myelodysplastic Syndrome/Acute Myeloid Leukemia

Myelodysplastic syndrome (MDS)/Acute Myeloid Leukemia (AML) has occurred in patients treated with Lynparza and some cases were fatal.

In clinical studies, among 2219 patients with various BRCAm, gBRCAm, HRR gene-mutated or HRD-positive cancers who received Lynparza as a single agent or as part of combination regimen, consistent with approved indications, the cumulative incidence of MDS/AML was approximately 1.2% (26/2219) [see Adverse Reactions (6.1)]. Of these, 54% (14/26) had a fatal outcome. The median duration of therapy with Lynparza in patients who developed MDS/AML was approximately 2 years (range: < 6 months to > 4 years). All of these patients had received previous chemotherapy with platinum agents and/or other DNA damaging agents including radiotherapy.

In SOLO1, patients with newly diagnosed advanced BRCAm ovarian cancer, the incidence of MDS/AML was 1.9% (5/260) in patients who received Lynparza and 0.8% (1/130) in patients who received placebo based on an updated analysis. In PAOLA-1, of patients with newly diagnosed advanced ovarian cancer with HRD-positive status, the incidence of MDS/AML was 1.6% (4/255) in patients who received Lynparza and 2.3% (3/131) in the control arm.

In SOLO2, patients with BRCAm platinum-sensitive relapsed ovarian cancer, the incidence of MDS/AML was 8% (15/195) in patients who received Lynparza and 4% (4/99) in patients who received placebo. The duration of Lynparza treatment prior to the diagnosis of MDS/AML ranged from 0.6 years to 4.5 years.

Do not start Lynparza until patients have recovered from hematological toxicity caused by previous chemotherapy (≤ Grade 1). Monitor complete blood count for cytopenia at baseline and monthly thereafter for clinically significant changes during treatment. For prolonged hematological toxicities, interrupt Lynparza and monitor blood counts weekly until recovery. If the levels have not recovered to Grade 1 or less after 4 weeks, refer the patient to a hematologist for further investigations, including bone marrow analysis and blood sample for cytogenetics. If MDS/AML is confirmed, discontinue Lynparza.

5.2 Pneumonitis

Pneumonitis, including severe and fatal cases, has occurred in patients treated with Lynparza.

In clinical studies, among patients who received Lynparza as a single agent or as part of a combination regimen [see Error! Hyperlink reference not valid.], the incidence of pneumonitis, including fatal cases, was 1.0% (29/2851).

If patients present with new or worsening respiratory symptoms such as dyspnea, cough and fever, or a radiological abnormality occurs, interrupt Lynparza treatment and promptly assess the source of the symptoms. If pneumonitis is confirmed, discontinue Lynparza treatment and treat the patient appropriately.

5.3 Venous Thromboembolism

Venous thromboembolism (VTE), including severe or fatal pulmonary embolism (PE), occurred in patients treated with Lynparza [see Adverse Reactions (6.1)].

In the combined data of two randomized, placebo-controlled clinical studies (PROfound and PROpel) in patients with metastatic castration-resistant prostate cancer (N=1180), VTE occurred in 8% of patients who received Lynparza, including pulmonary embolism in 6%. In the control arms, VTE occurred in 2.5% including pulmonary embolism in 1.5%.

Monitor patients for clinical signs and symptoms of venous thrombosis and pulmonary embolism and treat as medically appropriate, which may include long-term anticoagulation as clinically indicated.

5.4 Hepatotoxicity, Including Drug-Induced Liver Injury

Hepatotoxicity, including severe and potentially fatal cases of drug-induced liver injury (DILI), has occurred in patients treated with Lynparza [see Adverse Reactions (6.2)].

Evaluate bilirubin and transaminases at baseline and throughout treatment with Lynparza. For patients who develop abnormal liver tests after Lynparza, monitor more frequently for liver test abnormalities and clinical signs and symptoms of hepatic toxicity.

If DILI is suspected, withhold Lynparza. Upon confirmation of DILI, discontinue Lynparza.

5.5 Embryo-Fetal Toxicity

Lynparza can cause fetal harm when administered to a pregnant woman based on its mechanism of action and findings in animals. In an animal reproduction study, administration of olaparib to pregnant rats during the period of organogenesis caused teratogenicity and embryo-fetal toxicity at exposures below those in patients receiving the recommended human dose of 300 mg twice daily. Apprise pregnant women of the potential hazard to a fetus and the potential risk for loss of the pregnancy. Advise females of reproductive potential to use effective contraception during treatment and for 6 months following the last dose of Lynparza. Based on findings from genetic toxicity and animal reproduction studies, advise male patients with female partners of reproductive potential or who are pregnant to use effective contraception during treatment and for 3 months following the last dose of Lynparza [see Use in Specific Populations (8.1, 8.3)].

6 ADVERSE REACTIONS

The following adverse reactions are discussed elsewhere in the labeling:

- Myelodysplastic Syndrome/Acute Myeloid Leukemia [see Warnings and Precautions (5.1)]
- Pneumonitis [see Warnings and Precautions (5.2)]
- Venous Thromboembolism [see Warnings and Precautions (5.3)]
- Hepatotoxicity, Including Drug-Induced Liver Injury [see Warnings and Precautions (5.4)]

6.1 Clinical Trial Experience

Because clinical trials are conducted under widely varying conditions, adverse reaction rates observed in the clinical trials of a drug cannot be directly compared to rates in the clinical trials of another drug and may not reflect the rates observed in practice.

Unless otherwise specified, the data described in the WARNINGS AND PRECAUTIONS reflect exposure to Lynparza as a single agent or as part of a combination regimen (SOLO-1, SOLO-2, PAOLA-1, OlympiA, OlympiAD, POLO, PROfound, and PROpel) in 2851 patients that were pooled to conduct safety analyses.

Additional data reflect exposure to Lynparza as a single agent in 2901 patients; 2135 patients with exposure to 300 mg twice daily tablet dose including five controlled, randomized, trials (SOLO-1, SOLO-2, OlympiAD, POLO, and PROfound) and to 400 mg twice daily capsule dose in 766 patients in other trials that were pooled to conduct safety analyses.

In this pooled single agent safety population, 56% of patients were exposed for 6 months or longer and 28% were exposed for greater than one year in the Lynparza group.

In this pooled single agent safety population, the most common adverse reactions in ≥10% of patients were nausea (60%), fatigue (55%), anemia (36%), vomiting (32%), diarrhea (24%), decreased appetite (22%), headache (16%), dysgeusia (15%), cough (15%), neutropenia (14%), dyspnea (14%), dizziness (12%), dyspepsia (12%), leukopenia (11%), and thrombocytopenia (10%).

First-Line Maintenance Treatment of BRCA-mutated Advanced Ovarian Cancer

SOLO-1

The safety of Lynparza for the maintenance treatment of patients with BRCA-mutated advanced ovarian cancer following first-line treatment with platinum-based chemotherapy was investigated in SOLO-1 [see Clinical Studies (14.1)]. Patients received Lynparza tablets 300 mg orally twice daily (n=260) or placebo (n=130) until disease progression or unacceptable toxicity. The median duration of study treatment was 25 months for patients who received Lynparza and 14 months for patients who received placebo.

Among patients who received Lynparza, dose interruptions due to an adverse reaction of any grade occurred in 52% and dose reductions due to an adverse reaction occurred in 28%. The most frequent adverse reactions leading to dose interruption or reduction of Lynparza were anemia (23%), nausea (14%), and vomiting (10%). Discontinuation due to adverse reactions occurred in 12% of patients receiving Lynparza. The most frequent adverse reactions that led to discontinuation of Lynparza were fatigue (3.1%), anemia (2.3%), and nausea (2.3%).

Tables 2 and 3 summarize adverse reactions and laboratory abnormalities in SOLO-1.

Table 2 Adverse Reactions [Graded according to the National Cancer Institute Common Terminology Criteria for Adverse Events (NCI CTCAE), version 4.0.] in SOLO-1 (≥10% of Patients Who Received Lynparza)
Adverse Reaction | Lynparza tablets; n=260 |  | Placebo; n=130
Adverse Reaction | All Grades; (%) | Grades; 3 – 4 (%) | All; Grades (%) | Grades; 3 – 4 (%)
Gastrointestinal Disorders
Nausea | 77 | 1 | 38 | 0
Abdominal pain [Includes abdominal pain, abdominal pain lower, abdominal pain upper, abdominal distension, abdominal discomfort, and abdominal tenderness.] | 45 | 2 | 35 | 1
Vomiting | 40 | 0 | 15 | 1
Diarrhea [Includes colitis, diarrhea, and gastroenteritis.] | 37 | 3 | 26 | 0
Constipation | 28 | 0 | 19 | 0
Dyspepsia | 17 | 0 | 12 | 0
Stomatitis [Includes stomatitis, aphthous ulcer, and mouth ulceration.] | 11 | 0 | 2 | 0
General Disorders and Administration Site Conditions
Fatigue [Includes asthenia, fatigue, lethargy, and malaise.] | 67 | 4 | 42 | 2
Blood and Lymphatic System Disorders
Anemia | 38 | 21 | 9 | 2
Neutropenia [Includes neutropenia and febrile neutropenia.] | 17 | 6 | 7 | 3
Leukopenia [Includes leukopenia and white blood cell count decreased.] | 13 | 3 | 8 | 0
Thrombocytopenia [Includes platelet count decreased and thrombocytopenia.] | 11 | 1 | 4 | 2
Infections and Infestations
Upper respiratory tract infection/ influenza/nasopharyngitis/bronchitis | 28 | 0 | 23 | 0
UTI [Includes urosepsis, urinary tract infection, urinary tract pain, and pyuria.] | 13 | 1 | 7 | 0
Nervous System Disorders
Dysgeusia | 26 | 0 | 4 | 0
Dizziness | 20 | 0 | 15 | 1
Metabolism and Nutrition Disorders
Decreased appetite | 20 | 0 | 10 | 0
Respiratory, Thoracic and Mediastinal Disorders
Dyspnea [Includes dyspnea and dyspnea exertional.] | 15 | 0 | 6 | 0

Clinically relevant adverse reactions that occurred in <10% of patients receiving Lynparza were increased blood creatinine (8%), lymphopenia (6%), VTE (3%), hypersensitivity (2%), MDS/AML (1.9%), pneumonitis (1.9%), dermatitis (1%), and increased mean cell volume (0.4%).

Table 3 Laboratory Abnormalities Reported in ≥25% of Patients in SOLO-1
Laboratory; Parameter [Patients were allowed to enter clinical studies with laboratory values of CTCAE Grade 1.] | Lynparza tablets; n [This number represents the safety population. The derived values in the table are based on the total number of evaluable patients for each laboratory parameter.] =260 |  | Placebo; n=130
Laboratory; Parameter [Patients were allowed to enter clinical studies with laboratory values of CTCAE Grade 1.] | Grades 1-4; (%) | Grades 3-4; (%) | Grades 1-4; (%) | Grades 3-4; (%)
Decrease in hemoglobin | 87 | 19 | 63 | 2
Increase in mean corpuscular volume | 87 | - | 43 | -
Decrease in leukocytes | 70 | 7 | 52 | 1
Decrease in lymphocytes | 67 | 14 | 29 | 5
Decrease in absolute neutrophil count | 51 | 9 | 38 | 6
Decrease in platelets | 35 | 1 | 20 | 2
Increase in serum creatinine | 34 | 0 | 18 | 0

First-line Maintenance Treatment of HRD-positive Advanced Ovarian Cancer in Combination with Bevacizumab

PAOLA-1

The safety of Lynparza in combination with bevacizumab for the maintenance treatment of patients with advanced ovarian cancer following first-line treatment containing platinum-based chemotherapy and bevacizumab was investigated in PAOLA-1 [see Clinical Studies (14.2)]. This study was a placebo-controlled, double-blind study in which 802 patients received either Lynparza 300 mg BID in combination with bevacizumab (n=535) or placebo in combination with bevacizumab (n=267) until disease progression or unacceptable toxicity. The median duration of treatment with Lynparza was 17.3 months and 11 months for bevacizumab post-randomization on the Lynparza/bevacizumab arm.

Fatal adverse reactions occurred in 1 patient due to concurrent pneumonia and aplastic anemia. Serious adverse reactions occurred in 31% of patients who received Lynparza/bevacizumab. Serious adverse reactions in >5% of patients included hypertension (19%) and anemia (17%).

Dose interruptions due to an adverse reaction of any grade occurred in 54% of patients receiving Lynparza/bevacizumab and dose reductions due to an adverse reaction occurred in 41% of patients who received Lynparza/bevacizumab.

The most frequent adverse reactions leading to dose interruption in the Lynparza/bevacizumab arm were anemia (21%), nausea (7%), vomiting (3%), and fatigue (3%), and the most frequent adverse reactions leading to reduction in the Lynparza/bevacizumab arm were anemia (19%), nausea (7%), and fatigue (4%).

Discontinuation due to adverse reactions occurred in 20% of patients receiving Lynparza/bevacizumab. Specific adverse reactions that most frequently led to discontinuation in patients treated with Lynparza/bevacizumab were anemia (4%) and nausea (3%).

The most common adverse reactions (≥10%) for patients receiving Lynparza/bevacizumab irrespective of the frequency compared with the placebo/bevacizumab arm were nausea (53%), fatigue (including asthenia) (53%), anemia (41%), lymphopenia (24%), vomiting (22%), diarrhea (18%), neutropenia (18%), leukopenia (18%), urinary tract infection (15%), and headache (14%).

Tables 4 and 5 summarize adverse reactions and laboratory abnormalities in PAOLA-1, respectively.

Table 4 Adverse Reactions [Graded according to the National Cancer Institute Common Terminology Criteria for Adverse Events (NCI CTCAE), version 4.0.] Occurring in ≥10% of Patients Treated with Lynparza/bevacizumab in PAOLA-1 and at ≥5% Frequency Compared to the Placebo/bevacizumab Arm
Adverse Reactions | Lynparza/bevacizumab; n=535 |  | Placebo/bevacizumab n=267
Adverse Reactions | Grades 1-4; (%) | Grades 3-4; (%) | Grades 1-4; (%) | Grades 3-4; (%)
General Disorders and Administration Site Conditions
Fatigue (including asthenia) [Includes asthenia and fatigue.] | 53 | 5 | 32 | 1.5
Gastrointestinal Disorders
Nausea | 53 | 2.4 | 22 | 0.7
Vomiting | 22 | 1.7 | 11 | 1.9
Blood and Lymphatic Disorders
Anemia [Includes anemia, anemia macrocytic, erythropenia, haematocrit decreased, haemoglobin decreased, normochromic anemia, normochromic normocytic anemia, normocytic anemia, and red blood cell count decreased.] | 41 | 17 | 10 | 0.4
Lymphopenia [Includes B-lymphocyte count decreased, lymphocyte count decreased, lymphopenia, and T-lymphocyte count decreased.] | 24 | 7 | 9 | 1.1
Leukopenia [Includes leukopenia and white blood cell count decreased.] | 18 | 1.9 | 10 | 1.5

Clinically relevant adverse reactions that occurred in <10% of patients receiving Lynparza/bevacizumab were dysgeusia (8%), dyspnea (8%), stomatitis (5%), dyspepsia (4.3%), erythema (3%), dizziness (2.6%), hypersensitivity (1.7%), pneumonitis (0.9%), and MDS/AML (0.7%).

Venous thromboembolism occurred more commonly in patients receiving Lynparza/bevacizumab (5%) than in those receiving placebo/bevacizumab (1.9%).

Table 5 Laboratory Abnormalities Reported in ≥25% of Patients in PAOLA-1 [Reported within 30 days of the last dose.]
Laboratory Parameter [Patients were allowed to enter clinical studies with laboratory values of CTCAE Grade 1.] | Lynparza/bevacizumab n=535 |  | Placebo/bevacizumab n [This number represents the safety population. The derived values in the table are based on the total number of evaluable patients for each laboratory parameter.] =267
Laboratory Parameter [Patients were allowed to enter clinical studies with laboratory values of CTCAE Grade 1.] | Grades 1-4; (%) | Grades 3-4; (%) | Grades 1-4; (%) | Grades 3-4; (%)
Decrease in hemoglobin | 79 | 13 | 55 | 0.4
Decrease in lymphocytes | 63 | 10 | 42 | 3
Increase in serum creatinine | 61 | 0.4 | 36 | 0.4
Decrease in leukocytes | 59 | 3.4 | 45 | 2.2
Decrease in absolute neutrophil count | 35 | 7 | 30 | 3.7
Decrease in platelets | 35 | 2.4 | 28 | 0.4

Maintenance Treatment of BRCA-mutated Recurrent Ovarian Cancer

SOLO-2

The safety of Lynparza for the maintenance treatment of patients with platinum sensitive gBRCAm ovarian cancer was investigated in SOLO-2 [see Clinical Studies (14.3)]. Patients received Lynparza tablets 300 mg orally twice daily (n=195) or placebo (n=99) until disease progression or unacceptable toxicity. The median duration of study treatment was 19.4 months for patients who received Lynparza and 5.6 months for patients who received placebo.

Among patients who received Lynparza, dose interruptions due to an adverse reaction of any grade occurred in 45% and dose reductions due to an adverse reaction occurred in 27%. The most frequent adverse reactions leading to dose interruption or reduction of Lynparza were anemia (22%), neutropenia (9%), and fatigue/asthenia (8%). Discontinuation due to an adverse reaction occurred in 11% of patients receiving Lynparza.

Tables 6 and 7 summarize adverse reactions and laboratory abnormalities in SOLO-2.

Table 6 Adverse Reactions [Graded according to the National Cancer Institute Common Terminology Criteria for Adverse Events (NCI CTCAE), version 4.0.] in SOLO-2 (≥20% of Patients Who Received Lynparza)
Adverse Reaction | Lynparza tablets; n=195 |  | Placebo; n=99
Adverse Reaction | Grades 1-4; (%) | Grades 3-4; (%) | Grades 1-4; (%) | Grades 3-4; (%)
Gastrointestinal Disorders
Nausea | 76 | 3 | 33 | 0
Vomiting | 37 | 3 | 19 | 1
Diarrhea | 33 | 2 | 22 | 0
Stomatitis [Represents grouped term consisting of abscess oral, aphthous ulcer, gingival abscess, gingival disorder, gingival pain, gingivitis, mouth ulceration, mucosal infection, mucosal inflammation, oral candidiasis, oral discomfort, oral herpes, oral infection, oral mucosal erythema, oral pain, oropharyngeal discomfort, and oropharyngeal pain.] | 20 | 1 | 16 | 0
General Disorders and Administration Site Conditions
Fatigue including asthenia | 66 | 4 | 39 | 2
Blood and Lymphatic Disorders
Anemia [Represents grouped term consisting of anemia, hematocrit decreased, hemoglobin decreased, iron deficiency, mean cell volume increased, and red blood cell count decreased.] | 44 | 20 | 9 | 2
Infections and Infestations
Nasopharyngitis/URI/sinusitis/ rhinitis/influenza | 36 | 0 | 29 | 0
Musculoskeletal and Connective Tissue Disorders
Arthralgia/myalgia | 30 | 0 | 28 | 0
Nervous System Disorders
Dysgeusia | 27 | 0 | 7 | 0
Headache | 26 | 1 | 14 | 0
Metabolism and Nutrition Disorders
Decreased appetite | 22 | 0 | 11 | 0

Clinically relevant adverse reactions that occurred in <20% of patients receiving Lynparza were neutropenia (19%), cough (18%), leukopenia (16%), hypomagnesemia (14%), thrombocytopenia (14%), dizziness (13%), dyspepsia (11%), increased creatinine (11%), MDS/AML (8%), edema (8%), rash (6%), VTE (5%), pneumonitis (1%), and lymphopenia (1%).

Table 7 Laboratory Abnormalities Reported in ≥25% of Patients in SOLO-2
Laboratory Parameter [Patients were allowed to enter clinical studies with laboratory values of CTCAE Grade 1.] | Lynparza tablets; n [This number represents the safety population. The derived values in the table are based on the total number of evaluable patients for each laboratory parameter.] =195 |  | Placebo; n=99
Laboratory Parameter [Patients were allowed to enter clinical studies with laboratory values of CTCAE Grade 1.] | Grades 1-4; (%) | Grades 3-4; (%) | Grades 1-4; (%) | Grades 3-4; (%)
Increase in mean corpuscular volume [Represents the proportion of subjects whose mean corpuscular volume was > upper limit of normal (ULN).] | 89 | - | 52 | -
Decrease in hemoglobin | 83 | 17 | 69 | 0
Decrease in leukocytes | 69 | 5 | 48 | 1
Decrease in lymphocytes | 67 | 11 | 37 | 1
Decrease in absolute neutrophil count | 51 | 7 | 34 | 3
Increase in serum creatinine | 44 | 0 | 29 | 0
Decrease in platelets | 42 | 2 | 22 | 1

Adjuvant Treatment of germline BRCA-mutated HER2-negative High Risk Early Breast Cancer

OlympiA

The safety of Lynparza as monotherapy for the adjuvant treatment of patients with gBRCA-mutated HER2-negative high risk early breast cancer was investigated in OlympiA [see Clinical Studies (14.4)]. This study was a randomized, double-blind, multi-center study in which patients received either Lynparza tablets 300 mg orally twice daily (n=911) or placebo (n=904) for a total of 1 year, or until disease recurrence, or unacceptable toxicity. The median duration of treatment was 1 year in both arms.

Dose interruptions due to an adverse reaction of any grade occurred in 31% of patients receiving Lynparza; dose reductions due to an adverse reaction occurred in 23% of patients receiving Lynparza. The most frequent adverse reactions leading to dose interruption of Lynparza were anemia (11%), neutropenia (6%), nausea (5%), leukopenia (3.5%), fatigue (3%), and vomiting (2.9%) and the most frequent adverse reactions leading to dose reduction of Lynparza were anemia (8%), nausea (4.7%), neutropenia (4.2%), fatigue (3.3%), leukopenia (1.8%), and vomiting (1.5%). Discontinuation due to adverse reactions occurred in 10% of patients receiving Lynparza. The adverse reactions that most frequently led to discontinuation of Lynparza were nausea (2%), anemia (1.8%), and fatigue (1.3%).

Tables 8 and 9 summarize the adverse reactions and laboratory abnormalities, respectively, in patients in OlympiA.

Table 8 Adverse Reactions [Graded according to the National Cancer Institute Common Terminology Criteria for Adverse Events (NCI CTCAE), version 4.03] in OlympiA (≥ 10% of Patients Who Received Lynparza)
Adverse Reactions | Lynparza tablets; n=911 |  | Placebo; n=904
Adverse Reactions | Grades 1-4; (%) | Grades 3-4; (%) | Grades 1-4; (%) | Grades 3-4; (%)
Gastrointestinal Disorders
Nausea | 57 | 0.8 | 23 | 0
Vomiting | 23 | 0.7 | 8 | 0
Diarrhea | 18 | 0.3 | 14 | 0.3
Stomatitis [Includes aphthous ulcer, mouth ulceration, and stomatitis.] | 10 | 0.1 | 4.5 | 0
General Disorders and Administration Site Conditions
Fatigue (including asthenia) | 42 | 1.8 | 28 | 0.7
Blood and Lymphatic Disorders
Anemia [Includes anemia, anemia macrocytic, erythropenia, hematocrit decreased, hemoglobin decreased, normochromic anemia, normochromic normocytic anemia, normocytic anemia, and red blood cell count decreased.] | 24 | 9 | 3.9 | 0.3
Leukopenia [Includes leukopenia and white blood cell count decreased.] | 17 | 3 | 6 | 0.3
Neutropenia [Includes agranulocytosis, febrile neutropenia, granulocyte count decreased, granulocytopenia, idiopathic neutropenia, neutropenia, neutropenic infection, neutropenic sepsis, and neutrophil count decreased.] | 16 | 5 | 7 | 0.8
Nervous System Disorders
Headache | 20 | 0.2 | 17 | 0.1
Dysgeusia [Includes dysgeusia and taste disorder.] | 12 | 0 | 4.8 | 0
Dizziness | 11 | 0.1 | 7 | 0.1
Metabolism and Nutrition Disorders
Decreased appetite | 13 | 0.2 | 6 | 0

Clinically relevant adverse reactions that occurred in <10% of patients receiving Lynparza were cough (9.2%), lymphopenia (7%), dyspepsia (6%), upper abdominal pain (4.9%), rash (4.9%), dyspnea (4.2%), thrombocytopenia (4.2%), increase in creatinine (2%), hypersensitivity (0.9%), pneumonitis (0.8%), VTE (0.5%), dermatitis (0.5%), increase in mean corpuscular volume (0.2%), and MDS/AML (0.2%).

Table 9 Laboratory Abnormalities Reported in ≥25% of Patients in OlympiA
Laboratory Parameter [Patients were allowed to enter clinical studies with laboratory values of CTCAE Grade 1.] | Lynparza tablets; n [This number represents the safety population. The derived values in the table are based on the total number of evaluable patients for each laboratory parameter.] = 911 |  | Placebo; n=904
Laboratory Parameter [Patients were allowed to enter clinical studies with laboratory values of CTCAE Grade 1.] | Grades 1-4; (%) | Grades 3-4; (%) | Grades 1-4; (%) | Grades 3-4; (%)
Decrease in lymphocytes | 77 | 13 | 59 | 3.7
Increase in mean corpuscular volume [Represents the proportion of subjects whose mean corpuscular volume was > ULN.] | 67 | 0 | 4.8 | 0
Decrease in hemoglobin | 65 | 8 | 31 | 0.9
Decrease in leukocytes | 64 | 5 | 42 | 0.7
Decrease in absolute neutrophil count | 39 | 7 | 27 | 1.1

Germline BRCA-mutated HER2-negative Metastatic Breast Cancer

OlympiAD

The safety of Lynparza was evaluated in gBRCAm patients with HER2-negative metastatic breast cancer who had previously received up to two lines of chemotherapy for the treatment of metastatic disease in OlympiAD [see Clinical Studies (14.5)]. Patients received either Lynparza tablets 300 mg orally twice daily (n=205) or a chemotherapy (capecitabine, eribulin, or vinorelbine) of the healthcare provider’s choice (n=91) until disease progression or unacceptable toxicity. The median duration of study treatment was 8.2 months in patients who received Lynparza and 3.4 months in patients who received chemotherapy.

Among patients who received Lynparza, dose interruptions due to an adverse reaction of any grade occurred in 35% and dose reductions due to an adverse reaction occurred in 25%. Discontinuation due to an adverse reaction occurred in 5% of patients receiving Lynparza.

Tables 10 and 11 summarize the adverse reactions and laboratory abnormalities in OlympiAD.

Table 10 Adverse Reactions [Graded according to NCI CTCAE v4.0.] in OlympiAD (≥20% of Patients Who Received Lynparza)
Adverse Reaction | Lynparza tablets; n=205 |  | Chemotherapy; n=91
Adverse Reaction | Grades 1-4; (%) | Grades 3-4; (%) | Grades 1-4; (%) | Grades 3-4; (%)
Gastrointestinal Disorders
Nausea | 58 | 0 | 35 | 1
Vomiting | 30 | 0 | 15 | 1
Diarrhea | 21 | 1 | 22 | 0
Blood and Lymphatic Disorders
Anemia [Represents grouped terms consisting of anemia (anemia erythropenia, hematocrit decreased, hemoglobin decreased, and red blood cell count decreased).] | 40 | 16 | 26 | 4
Neutropenia [Represents grouped terms consisting of neutropenia (febrile neutropenia, granulocyte count decreased, granulocytopenia, neutropenia, neutropenic infection, neutropenic sepsis, and neutrophil count decreased).] | 27 | 9 | 50 | 26
Leukopenia [Represents grouped terms consisting of leukopenia (leukopenia and white blood cell count decreased).] | 25 | 5 | 31 | 13
General Disorders and Administration Site Conditions
Fatigue (including asthenia) | 37 | 4 | 36 | 1
Infections and Infestations
Respiratory tract infection [Represents grouped terms consisting of bronchitis, influenza, lower respiratory tract infection, nasopharyngitis, pharyngitis, respiratory tract infection, rhinitis, sinusitis, upper respiratory tract infection, and upper respiratory tract infection bacterial.] | 27 | 1 | 22 | 0
Nervous System Disorders
Headache | 20 | 1 | 15 | 2

Clinically relevant adverse reactions that occurred in <20% of patients receiving Lynparza were cough (18%), decreased appetite (16%), thrombocytopenia (11%), dysgeusia (9%), lymphopenia (8%), dyspepsia (8%), dizziness (7%), stomatitis (7%), upper abdominal pain (7%), rash (5%), increase in serum creatinine (3%), dermatitis (1%), and VTE (1%).

Table 11 Laboratory Abnormalities Reported in ≥25% of Patients in OlympiAD
Laboratory Parameter [Patients were allowed to enter clinical studies with laboratory values of CTCAE Grade 1.] | Lynparza tablets; n [This number represents the safety population. The derived values in the table are based on the total number of evaluable patients for each laboratory parameter.] = 205 |  | Chemotherapy; n= 91
Laboratory Parameter [Patients were allowed to enter clinical studies with laboratory values of CTCAE Grade 1.] | Grades 1-4; (%) | Grades 3-4; (%) | Grades 1-4; (%) | Grades 3-4; (%)
Decrease in hemoglobin | 82 | 17 | 66 | 3
Decrease in lymphocytes | 73 | 21 | 63 | 3
Decrease in leukocytes | 71 | 8 | 70 | 23
Increase in mean corpuscular volume [Represents the proportion of subjects whose mean corpuscular volume was > ULN.] | 71 | - | 33 | -
Decrease in absolute neutrophil count | 46 | 11 | 65 | 38
Decrease in platelets | 33 | 3 | 28 | 0

First-line Maintenance Treatment of Germline BRCA-mutated Metastatic Pancreatic Adenocarcinoma

POLO

The safety of Lynparza as maintenance treatment of germline BRCA-mutated metastatic pancreatic adenocarcinoma following first-line treatment with platinum-based chemotherapy was evaluated in POLO [see Clinical Studies (14.6)]. Patients received Lynparza tablets 300 mg orally twice daily (n=90) or placebo (n=61) until disease progression or unacceptable toxicity. Among patients receiving Lynparza, 34% were exposed for 6 months or longer and 25% were exposed for greater than one year.

Among patients who received Lynparza, dosage interruptions due to an adverse reaction of any grade occurred in 35% and dosage reductions due to an adverse reaction occurred in 17%. The most frequent adverse reactions leading to dosage interruption or reduction in patients who received Lynparza were anemia (11%), vomiting (5%), abdominal pain (4%), asthenia (3%), and fatigue (2%). Discontinuation due to adverse reactions occurred in 6% of patients receiving Lynparza. The most frequent adverse reaction that led to discontinuation of Lynparza was fatigue (2.2%).

Tables 12 and 13 summarize the adverse reactions and laboratory abnormalities in patients in POLO.

Table 12 Adverse Reactions [Graded according to NCI CTCAE, version 4.0.] in POLO (Occurring in ≥10% of Patients who Received Lynparza)
Adverse Reaction | Lynparza tablets (n=91) [This number represents the safety population. The derived values in the table are based on the total number of evaluable patients for each laboratory parameter.] |  | Placebo (n=60)
Adverse Reaction | All Grades (%) | Grades 3 – 4 (%) | All Grades (%) | Grades 3 – 4 (%)
General Disorders and Administration Site Conditions
Fatigue [Includes asthenia and fatigue.] | 60 | 5 | 35 | 2
Gastrointestinal Disorders
Nausea | 45 | 0 | 23 | 2
Abdominal pain [Includes abdominal pain, abdominal pain upper, and abdominal pain lower.] | 34 | 2 | 37 | 5
Diarrhea | 29 | 0 | 15 | 0
Constipation | 23 | 0 | 10 | 0
Vomiting | 20 | 1 | 15 | 2
Stomatitis [Includes stomatitis and mouth ulceration.] | 10 | 0 | 5 | 0
Blood and Lymphatic System Disorders
Anemia | 27 | 11 | 17 | 3
Thrombocytopenia [Includes platelets count decreased and thrombocytopenia.] | 14 | 3 | 7 | 0
Neutropenia [Includes neutropenia, febrile neutropenia, and neutrophil count decreased.] | 12 | 4 | 8 | 3
Metabolism and Nutrition Disorders
Decreased appetite | 25 | 3 | 7 | 0
Musculoskeletal and Connective Tissue Disorders
Back pain | 19 | 0 | 17 | 2
Arthralgia | 15 | 1 | 10 | 0
Skin and Subcutaneous Tissue Disorder
Rash [Includes rash erythematous, rash macular, and rash maculo-papular.] | 15 | 0 | 5 | 0
Respiratory, Thoracic and Mediastinal Disorders
Dyspnea [Includes dyspnea and dyspnea exertional.] | 13 | 0 | 5 | 2
Infections and Infestations
Nasopharyngitis | 12 | 0 | 3 | 0
Nervous System Disorders
Dysgeusia | 11 | 0 | 5 | 0

Clinically relevant adverse reactions that occurred in <10% of patients receiving Lynparza were cough (9%), abdominal pain upper (7%), blood creatinine increased (7%), dizziness (7%), headache (7%), dyspepsia (5%), leukopenia (5%), VTE (3%), hypersensitivity (2%), and lymphopenia (2%), and pneumonitis (1.1%).

Table 13 Laboratory Abnormalities Reported in ≥25% of Patients in POLO
Laboratory; Parameter [Patients were allowed to enter POLO with hemoglobin ≥9 g/dL (CTCAE Grade 2) and other laboratory values of CTCAE Grade 1.] | Lynparza tablets; n [This number represents the safety population. The derived values in the table are based on the total number of evaluable patients for each laboratory parameter.] =91 |  | Placebo; n=60
Laboratory; Parameter [Patients were allowed to enter POLO with hemoglobin ≥9 g/dL (CTCAE Grade 2) and other laboratory values of CTCAE Grade 1.] | Grades 1-4; (%) | Grades 3-4; (%) | Grades 1-4 (%) | Grades 3-4; (%)
Increase in serum creatinine | 99 | 2 | 85 | 0
Decrease in hemoglobin | 86 | 11 | 65 | 0
Increase in mean corpuscular volume [Represents the proportion of subjects whose mean corpuscular volume was > ULN.] | 71 | - | 30 | -
Decrease in lymphocytes | 61 | 9 | 27 | 0
Decrease in platelets | 56 | 2 | 39 | 0
Decrease in leukocytes | 50 | 3 | 23 | 0
Decrease in absolute neutrophil count | 25 | 3 | 10 | 0

HRR Gene-mutated Metastatic Castration-Resistant Prostate Cancer

PROfound

The safety of Lynparza as monotherapy was evaluated in patients with mCRPC and HRR gene mutations who have progressed following prior treatment with enzalutamide or abiraterone in PROfound [see Clinical Studies (14.7)]. This study was a randomized, open-label, multi-center study in which 386 patients received either Lynparza tablets 300 mg orally twice daily (n=256) or investigator’s choice of enzalutamide or abiraterone acetate (n=130) until disease progression or unacceptable toxicity. Among patients receiving Lynparza, 62% were exposed for 6 months or longer and 20% were exposed for greater than one year.

Fatal adverse reactions occurred in 4% of patients treated with Lynparza. These included pneumonia (1.2%), cardiopulmonary failure (0.4%), aspiration pneumonia (0.4%), intestinal diverticulum (0.4%), septic shock (0.4%), Budd-Chiari Syndrome (0.4%), sudden death (0.4%), and acute cardiac failure (0.4%).

Serious adverse reactions occurred in 36% of patients receiving Lynparza. The most frequent serious adverse reactions (≥2%) were anemia (9%), pneumonia (4%), pulmonary embolism (2%), fatigue/asthenia (2%), and urinary tract infection (2%).

Dose interruptions due to an adverse reaction of any grade occurred in 45% of patients receiving Lynparza; dose reductions due to an adverse reaction occurred in 22% of Lynparza patients. The most frequent adverse reactions leading to dose interruption of Lynparza were anemia (25%) and thrombocytopenia (6%) and the most frequent adverse reaction leading to reduction of Lynparza was anemia (16%). Discontinuation due to adverse reactions occurred in 18% of Lynparza. The adverse reaction that most frequently led to discontinuation of Lynparza was anemia (7%).

Tables 14 and 15 summarize the adverse reactions and laboratory abnormalities, respectively, in patients in PROfound.

Table 14 Adverse Reactions [Graded according to the National Cancer Institute Common Terminology Criteria for Adverse Events (NCI CTCAE), version 4.03.] Reported in ≥10% of Patients in PROfound
Adverse Reactions | Lynparza tablets; n=256 |  | Enzalutamide or abiraterone; n=130
Adverse Reactions | Grades 1-4; (%) | Grades 3-4; (%) | Grades 1-4; (%) | Grades 3-4; (%)
Blood and lymphatic disorders
Anemia [Includes anemia and hemoglobin decreased.] | 46 | 21 | 15 | 5
Thrombocytopenia [Includes platelet count decreased and thrombocytopenia.] | 12 | 4 | 3 | 0
Gastrointestinal disorders
Nausea | 41 | 1 | 19 | 0
Diarrhea | 21 | 1 | 7 | 0
Vomiting | 18 | 2 | 12 | 1
General disorders and administration site conditions
Fatigue (including asthenia) | 41 | 3 | 32 | 5
Metabolism and nutrition disorders
Decreased appetite | 30 | 1 | 18 | 1
Respiratory, thoracic, and mediastinal disorders
Cough | 11 | 0 | 2 | 0
Dyspnea | 10 | 2 | 3 | 0

Clinically relevant adverse reactions that occurred in <10% of patients receiving Lynparza were neutropenia (9%), VTE (7%), dizziness (7%), dysgeusia (7%), dyspepsia (7%), headache (6%), pneumonia (5%), stomatitis (5%), rash (4%), blood creatinine increase (4%), pneumonitis (2%), upper abdominal pain (2%), and hypersensitivity (1%).

Table 15 Laboratory Abnormalities Reported in ≥25% of Patients in PROfound
Laboratory Parameter [Patients were allowed to enter clinical studies with laboratory values of CTCAE Grade 1.] | Lynparza tablets; n [This number represents the safety population. The derived values in the table are based on the total number of evaluable patients for each laboratory parameter.] = 256 |  | Enzalutamide or abiraterone; n=130
Laboratory Parameter [Patients were allowed to enter clinical studies with laboratory values of CTCAE Grade 1.] | Grades 1-4; (%) | Grades 3-4; (%) | Grades 1-4; (%) | Grades 3-4; (%)
Decrease in hemoglobin | 98 | 13 | 73 | 4
Decrease in lymphocytes | 62 | 23 | 34 | 13
Decrease in leukocytes | 53 | 4 | 21 | 0
Decrease in absolute neutrophil count | 34 | 3 | 9 | 0

Treatment of BRCA-mutated Metastatic Castration-Resistant Prostate Cancer in Combination with Abiraterone and Prednisone or Prednisolone

PROpel

The safety of Lynparza in combination with abiraterone and prednisone or prednisolone for the treatment of patients in the first-line mCRPC setting was investigated in PROpel [see Clinical Studies (14.8)]. Patients were randomized to receive either Lynparza tablets 300 mg orally twice daily plus abiraterone tablets 1000 mg once daily (Lynparza/abiraterone) (n=398), or placebo plus abiraterone 1000 mg once daily (placebo/abiraterone) (n=396) until disease progression or unacceptable toxicity. Patients in both arms also received either prednisone or prednisolone 5 mg twice daily.

Fatal adverse reactions occurred in 6% of patients, including COVID-19 (3%) and pneumonias (0.5%).

Serious adverse reactions occurred in 39% of patients. Serious adverse reactions reported in > 2% of patients included anemia (6%), COVID-19 (6%), pneumonia (4.5%), pulmonary embolism (3.5%), and urinary tract infection (3%).

Permanent discontinuation of Lynparza due to adverse reactions occurred in 16% of patients treated in the Lynparza with abiraterone arm. The most common adverse reactions which resulted in permanent discontinuation of Lynparza were anemia (4.3%) and pneumonia (1.5%).

Dosage interruption of Lynparza due to adverse reactions occurred in 48% of patients treated in the Lynparza with abiraterone arm. The most common (>2%) adverse reactions requiring dosage interruption of Lynparza were anemia (16%), COVID-19 (6%) fatigue (3.5%), nausea (2.8%), pulmonary embolism (2.3%), and diarrhea (2.3%).

Dose reduction of Lynparza due to adverse reactions occurred in 21% of patients treated in the Lynparza with abiraterone arm. The most common (>2%) adverse reactions requiring dosage reductions of Lynparza were anemia (11%) and fatigue (2.5%).

The most common adverse reactions (≥10%) in patients who received Lynparza/abiraterone were anemia (48%), fatigue (38%), nausea (30%), diarrhea (19%), decreased appetite (16%), lymphopenia (14%), dizziness (14%), and abdominal pain (13%).

Tables 16 and 17 summarize adverse reactions and laboratory abnormalities in PROpel, respectively.

Table 16 Adverse Reactions (≥10%) in Patients Who Received Lynparza (with a Difference of ≥5% Compared to Placebo) in PROpel
Adverse Reactions [Graded according to the National Cancer Institute Common Terminology Criteria for Adverse Events (NCI CTCAE), version 4.03.] | Lynparza/abiraterone n=398 |  | Placebo/abiraterone n=396
Adverse Reactions [Graded according to the National Cancer Institute Common Terminology Criteria for Adverse Events (NCI CTCAE), version 4.03.] | Grades 1-4; (%) | Grades 3-4; (%) | Grades 1-4; (%) | Grades 3-4; (%)
Blood and Lymphatic Disorders
Anemia [Includes anemia, anemia macrocytic, and red blood cell count decreased] | 48 | 16 | 18 | 3.3
Lymphopenia [Includes lymphocyte count decreased and lymphopenia] | 14 | 5 | 6 | 1.8
General Disorders and Administration Site Conditions
Fatigue (including asthenia) | 38 | 2.3 | 30 | 1.5
Gastrointestinal Disorders
Nausea | 30 | 0.3 | 14 | 0.3
Diarrhea | 19 | 1 | 10 | 0.3
Abdominal pain [Includes abdominal discomfort, abdominal pain, abdominal pain upper, and abdominal pain lower] | 13 | 0 | 7 | 0.5
Metabolism and nutrition disorders
Decreased appetite | 16 | 1 | 7 | 0
Nervous System Disorders
Dizziness [Includes dizziness and vertigo.] | 14 | 0.3 | 7 | 0

Clinically relevant adverse reactions that occurred in <10% for patients receiving Lynparza plus abiraterone were headache (9%), VTE (8%), rash (7%), dysgeusia (6%), acute kidney injury (3%), stomatitis (2.5%), and pneumonitis (1%).

Table 17 Selected Laboratory Abnormalities Reported in ≥20% of Patients in PROpel
Laboratory Parameter | Lynparza/abiraterone n=398 [This number represents the safety population. The derived values in the table are based on the total number of evaluable patients for each laboratory parameter.] |  | Placebo/abiraterone n=396
Laboratory Parameter | Grades 1-4; (%) | Grades 3-4; (%) | Grades 1-4; (%) | Grades 3-4; (%)
Decrease in hemoglobin | 97 | 12 | 81 | 1.3
Decrease in lymphocytes | 70 | 23 | 49 | 11
Decrease in platelets | 23 | 1.2 | 20 | 0.3
Decrease in absolute neutrophil count | 23 | 5 | 6 | 0

6.2 Postmarketing Experience

The following adverse reactions have been identified during post-approval use of Lynparza. Because these reactions are reported voluntarily from a population of uncertain size, it is not always possible to reliably estimate their frequency or establish a causal relationship to drug exposure.

Hepatobiliary Disorders: Drug-induced liver injury.

Immune System Disorders: Hypersensitivity including angioedema.

Skin and Subcutaneous Tissue Disorders: Erythema nodosum, rash, dermatitis.

7 DRUG INTERACTIONS

7.1 Use with Anticancer Agents

Clinical studies of Lynparza with other myelosuppressive anticancer agents, including DNA damaging agents, indicate a potentiation and prolongation of myelosuppressive toxicity.

7.2 Effect of Other Drugs on Lynparza

Strong and Moderate CYP3A Inhibitors

Coadministration of CYP3A inhibitors can increase olaparib concentrations, which may increase the risk for adverse reactions [see Clinical Pharmacology (12.3)]. Avoid coadministration of strong or moderate CYP3A inhibitors. If the strong or moderate inhibitor must be coadministered, reduce the dose of Lynparza [see Dosage and Administration (2.4)].

Strong and Moderate CYP3A Inducers

Concomitant use with a strong or moderate CYP3A inducer decreased olaparib exposure, which may reduce Lynparza efficacy [see Clinical Pharmacology (12.3)]. Avoid coadministration of strong or moderate CYP3A inducers.

8 USE IN SPECIFIC POPULATIONS

8.1 Pregnancy

Risk Summary

Based on findings in animals and its mechanism of action [see Clinical Pharmacology (12.1)], Lynparza can cause fetal harm when administered to a pregnant woman. There are no available data on Lynparza use in pregnant women to inform the drug-associated risk. In an animal reproduction study, the administration of olaparib to pregnant rats during the period of organogenesis caused teratogenicity and embryo-fetal toxicity at exposures below those in patients receiving the recommended human dose of 300 mg twice daily (see Data). Apprise pregnant women of the potential hazard to the fetus and the potential risk for loss of the pregnancy.

The estimated background risk of major birth defects and miscarriage for the indicated population is unknown. The estimated background risk in the U.S. general population of major birth defects is 2-4%; and the risk for spontaneous abortion is approximately 15-20% in clinically recognized pregnancies.

Data

Animal Data

In a fertility and early embryonic development study in female rats, olaparib was administered orally for 14 days before mating through to Day 6 of pregnancy, which resulted in increased post-implantation loss at a dose level of 15 mg/kg/day (with maternal systemic exposures approximately 7% of the human exposure (AUC0-24h) at the recommended dose).

In an embryo-fetal development study, pregnant rats received oral doses of 0.05 and 0.5 mg/kg/day olaparib during the period of organogenesis. A dose of 0.5 mg/kg/day (with maternal systemic exposures approximately 0.18% of human exposure (AUC0-24h) at the recommended dose) caused embryo-fetal toxicities including increased post-implantation loss and major malformations of the eyes (anophthalmia, microphthalmia), vertebrae/ribs (extra rib or ossification center; fused or absent neural arches, ribs, and sternebrae), skull (fused exoccipital), and diaphragm (hernia). Additional abnormalities or variants included incomplete or absent ossification (vertebrae/sternebrae, ribs, limbs) and other findings in the vertebrae/sternebrae, pelvic girdle, lung, thymus, liver, ureter, and umbilical artery. Some findings noted above in the eyes, ribs, and ureter were observed at a dose of 0.05 mg/kg/day olaparib at lower incidence.

8.2 Lactation

Risk Summary

No data are available regarding the presence of olaparib in human milk, or on its effects on the breastfed infant or on milk production. Because of the potential for serious adverse reactions in the breastfed infants from Lynparza, advise a lactating woman not to breastfeed during treatment with Lynparza and for one month after receiving the last dose.

8.3 Females and Males of Reproductive Potential

Lynparza can cause fetal harm when administered to a pregnant woman [see Use in Specific Populations (8.1)].

Pregnancy Testing

Verify pregnancy status in females of reproductive potential prior to initiating treatment with Lynparza.

Contraception

Females

Advise females of reproductive potential to use effective contraception during treatment with Lynparza and for 6 months following the last dose.

Males

Based on findings in genetic toxicity and animal reproduction studies, advise male patients with female partners of reproductive potential or who are pregnant to use effective contraception during treatment and for 3 months following the last dose of Lynparza. Advise male patients not to donate sperm during therapy and for 3 months following the last dose of Lynparza [see Use in Specific Populations (8.1) and Nonclinical Toxicology (13.1)].

8.4 Pediatric Use

Safety and effectiveness of Lynparza have not been established in pediatric patients.

8.5 Geriatric Use

Of the 2901 patients with advanced solid tumors who received Lynparza as a single agent, 680 (23%) patients were aged ≥65 years, and this included 206 (7%) patients who were aged ≥75 years. Thirteen (0.4%) patients were aged ≥85 years.

Of the 535 patients with advanced solid tumors who received Lynparza tablets 300 mg orally twice daily in combination with bevacizumab (PAOLA-1), 204 (38%) patients were aged ≥65 years, and this included 31 (6%) patients who were aged ≥75 years.

Of the 398 patients with advanced solid tumors who received Lynparza tablets 300 mg orally twice daily in combination with abiraterone and prednisone or prednisolone (PROpel), 268 (67%) patients were aged ≥65 years, and this included 95 (24%) patients who were aged ≥75 years.

No overall differences in the safety or effectiveness of Lynparza were observed between these patients and younger patients.

8.6 Renal Impairment

No dosage modification is recommended in patients with mild renal impairment (CLcr 51 to 80 mL/min estimated by Cockcroft-Gault). Reduce Lynparza dosage to 200 mg twice daily in patients with moderate renal impairment (CLcr 31 to 50 mL/min) [see Dosage and Administration (2.5)]. There are no data in patients with severe renal impairment or end-stage disease (CLcr ≤30 mL/min) [see Clinical Pharmacology (12.3)].

8.7 Hepatic Impairment

No adjustment to the starting dose is required in patients with mild or moderate hepatic impairment (Child-Pugh classification A and B). There are no data in patients with severe hepatic impairment (Child-Pugh classification C) [see Clinical Pharmacology (12.3)].

11 DESCRIPTION

Olaparib is a poly (ADP-ribose) polymerase (PARP) inhibitor. The chemical name is 4-[(3-{[4-(cyclopropylcarbonyl)piperazin-1-yl]carbonyl}-4-fluorophenyl)methyl]phthalazin-1(2H)-one. The empirical molecular formula for Lynparza is C24H23FN4O3 and the relative molecular mass is 434.46. It has the following chemical structure:

Olaparib is a crystalline solid, is non-chiral and shows pH-independent low solubility across the physiological pH range.

Lynparza (olaparib) tablets for oral use contain 100 mg or 150 mg of olaparib. Inactive ingredients in the tablet core are copovidone, mannitol, colloidal silicon dioxide, and sodium stearyl fumarate. The tablet coating consists of hypromellose, polyethylene glycol 400, titanium dioxide, ferric oxide yellow, and ferrosoferric oxide (150 mg tablet only).

12 CLINICAL PHARMACOLOGY

12.1 Mechanism of Action

Olaparib is an inhibitor of poly (ADP-ribose) polymerase (PARP) enzymes, including PARP1, PARP2, and PARP3. PARP enzymes are involved in normal cellular functions, such as DNA transcription and DNA repair. Olaparib has been shown to inhibit growth of select tumor cell lines in vitro and decrease tumor growth in mouse xenograft models of human cancer, both as monotherapy or following platinum-based chemotherapy. Increased cytotoxicity and anti-tumor activity following treatment with olaparib were noted in cell lines and mouse tumor models with deficiencies in BRCA1/2, ATM, or other genes involved in the homologous recombination repair (HRR) of DNA damage and correlated with platinum response. In vitro studies have shown that olaparib-induced cytotoxicity may involve inhibition of PARP enzymatic activity and increased formation of PARP-DNA complexes, resulting in DNA damage and cancer cell death. In prostate cancer models, PARP1 has been shown to contribute to androgen receptor (AR) activity regulation; the combination of olaparib and AR inhibition resulted in cytotoxicity in vitro and anti-tumor activity in mouse xenograft models.

12.2 Pharmacodynamics

Cardiac Electrophysiology

The effect of olaparib on cardiac repolarization was assessed in 119 patients following a single dose of 300 mg and in 109 patients following multiple dosing of 300 mg twice daily. No clinically relevant effect of olaparib on QT interval was observed.

12.3 Pharmacokinetics

The area under the curve (AUC) of olaparib increases approximately proportionally following administration of single doses of 25 mg to 450 mg (0.08 to 1.5 times the recommended dose) and maximal concentrations (Cmax) increased slightly less than proportionally for the same dose range. Olaparib showed time-dependent pharmacokinetics and an AUC mean accumulation ratio of 1.8 is observed at steady state following a dose of 300 mg twice daily.

The mean (CV%) olaparib Cmax is 5.4 μg/mL (32%) and AUC is 39.2 μg*h/mL (44%) following a single 300 mg dose. The mean steady state olaparib Cmax and AUC is 7.6 μg/mL (35%) and 49.2 μg*h/mL (44%), following a dose of 300 mg twice daily.

Absorption

Following oral administration of olaparib, the median time to peak plasma concentration is 1.5 hours.

Effect of Food

Co-administration of a high fat and high calorie meal (800-1000 kcal, 50% of the calorie content made up from fat) with olaparib slowed the rate (tmax delayed by 2.5 hours) of absorption, but did not significantly alter the extent of olaparib absorption (mean AUC increased by approximately 8%).

Distribution

The mean (± standard deviation) apparent volume of distribution of olaparib is 158 ± 136 L following a single 300 mg dose of Lynparza. The protein binding of olaparib is approximately 82% in vitro.

Elimination

The mean (± standard deviation) terminal plasma half-life of olaparib is 14.9 ± 8.2 hours and the apparent plasma clearance is 7.4 ± 3.9 L/h following a single 300 mg dose of Lynparza.

Metabolism

Olaparib is metabolized by cytochrome P450 (CYP) 3A in vitro.

Following an oral dose of radiolabeled olaparib to female patients, unchanged olaparib accounted for 70% of the circulating radioactivity in plasma. It was extensively metabolized with unchanged drug accounting for 15% and 6% of radioactivity in urine and feces, respectively. The majority of the metabolism is attributable to oxidation reactions with a number of the components produced undergoing subsequent glucuronide or sulfate conjugation.

Excretion

Following a single dose of radiolabeled olaparib, 86% of the dosed radioactivity was recovered within a 7-day collection period, 44% via the urine and 42% via the feces. The majority of the material was excreted as metabolites.

Specific Populations

Patients with Renal Impairment

In a renal impairment trial, the mean AUC increased by 24% and Cmax by 15%, when olaparib was dosed in patients with mild renal impairment (CLcr=51-80 mL/min defined by the Cockcroft-Gault equation; n=13) and by 44% and 26%, respectively, when olaparib was dosed in patients with moderate renal impairment (CLcr=31-50 mL/min; n=13), compared to those with normal renal function (CLcr ≥81 mL/min; n=12). There was no evidence of a relationship between the extent of plasma protein binding of olaparib and creatinine clearance. There are no data in patients with severe renal impairment or end-stage renal disease (CLcr ≤30 mL/min).

Patients with Hepatic Impairment

In a hepatic impairment trial, the mean AUC increased by 15% and the mean Cmax increased by 13% when olaparib was dosed in patients with mild hepatic impairment (Child-Pugh classification A; n=10) and the mean AUC increased by 8% and the mean Cmax decreased by 13% when olaparib was dosed in patients with moderate hepatic impairment (Child-Pugh classification B; n=8), compared to patients with normal hepatic function (n=13). Hepatic impairment has no effect on the protein binding of olaparib and, therefore, total plasma exposure was representative of free drug. There are no data in patients with severe hepatic impairment (Child-Pugh classification C).

Drug Interaction Studies

Clinical Studies

CYP3A Inhibitors: Concomitant use of itraconazole (strong CYP3A inhibitor) increased olaparib Cmax by 42% and AUC by 170%. Concomitant use of fluconazole (moderate CYP3A inhibitor) is predicted to increase olaparib Cmax by 14% and AUC by 121%.

CYP3A Inducers: Concomitant use of rifampicin (strong CYP3A inducer) decreased olaparib Cmax by 71% and AUC by 87%. Concomitant use of efavirenz (moderate CYP3A inducer) is predicted to decrease olaparib Cmax by 31% and AUC by 60%.

In vitro Studies

CYP Enzymes: Olaparib is both an inhibitor and inducer of CYP3A and an inducer of CYP2B6. Olaparib is predicted to be a weak CYP3A inhibitor in humans.

UGT Enzymes: Olaparib is an inhibitor of UGT1A1.

Transporters: Olaparib is an inhibitor of BCRP, OATP1B1, OCT1, OCT2, OAT3, MATE1, and MATE2K. Olaparib is a substrate and inhibitor of the efflux transporter P-gp. The potential for olaparib to induce P-gp has not been evaluated.

13 NONCLINICAL TOXICOLOGY

13.1 Carcinogenesis, Mutagenesis, Impairment of Fertility

Carcinogenicity studies have not been conducted with olaparib.

Olaparib was clastogenic in an in vitro chromosomal aberration assay in mammalian Chinese hamster ovary (CHO) cells and in an in vivo rat bone marrow micronucleus assay. This clastogenicity is consistent with genomic instability resulting from the primary pharmacology of olaparib and indicates potential for genotoxicity in humans. Olaparib was not mutagenic in a bacterial reverse mutation (Ames) test.

In a fertility study, female rats received oral olaparib at doses of 0.05, 0.5, and 15 mg/kg/day for at least 14 days before mating through the first week of pregnancy. There were no adverse effects on mating and fertility rates at doses up to 15 mg/kg/day (maternal systemic exposures approximately 7% of the human exposure (AUC0-24h) at the recommended dose).

In a male fertility study, olaparib had no effect on mating and fertility in rats at oral doses up to 40 mg/kg/day following at least 70 days of olaparib treatment (with systemic exposures of approximately 5% of the human exposure (AUC0-24h) at the recommended dose).

14 CLINICAL STUDIES

14.1 First-Line Maintenance Treatment of BRCA-mutated Advanced Ovarian Cancer

The efficacy of Lynparza was evaluated in SOLO-1 (NCT01844986), a randomized (2:1), double-blind, placebo-controlled, multi-center trial in patients with BRCA-mutated advanced ovarian, fallopian tube, or primary peritoneal cancer following first-line platinum-based chemotherapy. Patients were randomized to receive Lynparza tablets 300 mg orally twice daily or placebo. Treatment was continued for up to 2 years or until disease progression or unacceptable toxicity; however, patients with evidence of disease at 2 years, who in the opinion of the treating healthcare provider could derive further benefit from continuous treatment, could be treated beyond 2 years. Randomization was stratified by response to first-line platinum-based chemotherapy (complete or partial response). The major efficacy outcome was investigator-assessed progression-free survival (PFS) evaluated according to Response Evaluation Criteria in Solid Tumors (RECIST), version 1.1.

A total of 391 patients were randomized, 260 to Lynparza and 131 to placebo. The median age of patients treated with Lynparza was 53 years (range: 29 to 82) and 53 years (range: 31 to 84) among patients on placebo. The ECOG performance status (PS) was 0 in 77% of patients receiving Lynparza and 80% of patients receiving placebo. Of all patients, 82% were White, 36% were enrolled in the U.S. or Canada, and 82% were in complete response to their most recent platinum-based regimen. The majority of patients (n=389) had germline BRCA mutation (gBRCAm), and 2 patients had somatic BRCAm (sBRCAm).

Of the 391 patients randomized in SOLO-1, 386 were retrospectively or prospectively tested with a Myriad BRACAnalysis test and 383 patients were confirmed to have deleterious or suspected deleterious gBRCAm status; 253 were randomized to the Lynparza arm and 130 to the placebo arm. Two out of 391 patients randomized in SOLO-1 were confirmed to have sBRCAm based on an investigational Foundation Medicine tissue test.

SOLO-1 demonstrated a statistically significant improvement in investigator-assessed PFS for Lynparza compared to placebo. Results from a blinded independent review were consistent. At the time of the analysis of PFS, overall survival (OS) data were not mature (21% of patients had died). Efficacy results are presented in Table 18 and Figure 1.

Table 18 Efficacy Results - SOLO-1 (Investigator Assessment)
 | Lynparza tablets; (n=260) | Placebo; (n=131)
Progression-Free Survival [Median follow-up of 41 months in both treatment arms.]
Number of events (%) | 102 (39%) | 96 (73%)
Median, months | NR | 13.8
Hazard ratio [A value <1 favors Lynparza. Hazard ratio from a Cox proportional hazards model including response to previous platinum chemotherapy (complete response versus partial response) as a covariate.] (95% CI) | 0.30 (0.23, 0.41)
p-value [The p-value is derived from a stratified log-rank test.] | <0.0001
NR not reached; CI Confidence Interval.

Figure 1 Kaplan-Meier Curves of Investigator-Assessed Progression-Free Survival - SOLO-1

14.2 First-line Maintenance Treatment of HRD-positive Advanced Ovarian Cancer in Combination with Bevacizumab

PAOLA-1 (NCT02477644) was a randomized, double-blind, placebo-controlled, multi-center trial that compared the efficacy of Lynparza in combination with bevacizumab versus placebo/bevacizumab for the maintenance treatment of advanced high-grade epithelial ovarian cancer, fallopian tube or primary peritoneal cancer following first-line platinum-based chemotherapy and bevacizumab. Randomization was stratified by first-line treatment outcome (timing and outcome of cytoreductive surgery and response to platinum-based chemotherapy) and tBRCAm status, determined by prospective local testing. All available clinical samples were retrospectively tested with Myriad myChoice® CDx. Patients were required to have no evidence of disease (NED) due to complete surgical resection, or who were in complete response (CR), or partial response (PR) following completion of first-line platinum-containing chemotherapy and bevacizumab. Patients were randomized (2:1) to receive Lynparza tablets 300 mg orally twice daily in combination with bevacizumab (n=537) 15 mg/kg every three weeks or placebo/bevacizumab (n=269). Patients continued bevacizumab in the maintenance setting and started treatment with Lynparza after a minimum of 3 weeks and up to a maximum of 9 weeks following completion of their last dose of chemotherapy. Lynparza treatment was continued for up to 2 years or until progression of the underlying disease or unacceptable toxicity. Patients who in the opinion of the treating physician could derive further benefit from continuous treatment could be treated beyond 2 years. Treatment with bevacizumab was for a total of up to 15 months, including the period given with chemotherapy and given as maintenance.

The major efficacy outcome measure was investigator-assessed PFS evaluated according to RECIST, version 1.1. An additional efficacy endpoint was overall survival (OS).

A statistically significant difference in PFS was observed in the intent-to-treat (ITT) population. Planned exploratory analyses of PFS and OS were conducted in patients with known HRD status. The PFS hazard ratio (HR) for patients with HRD-negative tumors (277/806; 34%) was 1.00 (95% CI: 0.75, 1.34) and the OS HR was 1.18 (95% CI: 0.87, 1.60) indicating that the clinical benefit was primarily attributed to the results seen in the HRD-positive population. Efficacy results in patients with HRD-positive tumors are summarized in Table 19, Figure 2, and Figure 3.

Among the 387 patients (48%) with HRD-positive tumors identified post-randomization using the Myriad myChoice® HRD Plus tumor test the median age was 58 years in both arms (range 32-82). Ovarian cancer was the primary tumor type in 87% of patients in both arms. Ninety five percent (95%) were serous histological type. The ECOG performance score was 0 in 75% of patients and 1 in 24% of patients. All patients had received first-line platinum-based therapy and bevacizumab. First-line treatment outcomes at screening indicated that patients had no evidence of disease with complete macroscopic resection at initial debulking surgery (36%), no evidence of disease/CR with complete macroscopic resection at interval debulking surgery (29%, both arms), no evidence of disease/CR in patients who had either incomplete resection (at initial or interval debulking surgery) or no debulking surgery (16%, both arms) and patients with a partial response (19%, both arms). Sixty-two (62%) of patients in the Lynparza/bevacizumab arm and 58% of patients in placebo/bevacizumab arm had tumors with a deleterious BRCA mutation. Patients were not restricted by the surgical outcome with 67% having complete cytoreduction at initial or interval debulking surgery and 33% having residual macroscopic disease.

Table 19 Efficacy Results - PAOLA-1 (HRD-positive status, Investigator Assessment)
 | Lynparza/bevacizumab; (n=255) | Placebo/bevacizumab; (n=132)
Progression-Free Survival [Results from a blinded independent review of PFS were consistent with those from investigator-assessed PFS]
Number of events (%) | 87 (34%) | 92 (70%)
Median, months | 37.2 | 17.7
Hazard ratio [The analysis was performed using an unstratified Cox proportional hazards model.] (95% CI) | 0.33 (0.25, 0.45)
Overall Survival [Based on final OS subgroup analysis.]
Number of events (%) | 93 (36%) | 69 (52%)
Median, months | 75.2 | 57.3
Hazard ratio† (95% CI) | 0.62 (0.45, 0.85)
CI Confidence interval.

Figure 2 Kaplan-Meier Curves of Investigator-Assessed Progression-Free Survival – PAOLA-1 (HRD-positive status)

Figure 3 Kaplan-Meier Curves of Overall Survival – PAOLA-1 (HRD-positive status)*

* Based on final OS subgroup analysis.

14.3 Maintenance Treatment of BRCA-mutated Recurrent Ovarian Cancer

The efficacy of Lynparza was evaluated in SOLO-2 (NCT01874353), a randomized (2:1) double-blind, placebo-controlled trial in patients with BRCAm ovarian, fallopian tube, or primary peritoneal cancer who were in response to platinum-based therapy. Patients were randomized to Lynparza tablets 300 mg orally twice daily or placebo until unacceptable toxicity or progressive disease. Randomization was stratified by response to last platinum chemotherapy (complete versus partial) and time to disease progression in the penultimate platinum-based chemotherapy prior to enrollment (6-12 months versus >12 months). All patients had received at least two prior platinum-containing regimens and were in response (complete or partial) to their most recent platinum-based regimen. The major efficacy outcome measure was investigator-assessed PFS evaluated according to RECIST, version 1.1. An additional efficacy outcome measure was OS.

A total of 295 patients were randomized, 196 to Lynparza and 99 to placebo. The median age of patients treated with Lynparza was 56 years (range: 28 to 83) and 56 years (range: 39 to 78) among patients treated with placebo. The ECOG PS was 0 in 83% of patients receiving Lynparza and 78% of patients receiving placebo. Of all patients, 89% were White, 17% were enrolled in the U.S. or Canada, 47% were in complete response to their most recent platinum-based regimen, and 40% had a progression-free interval of 6-12 months since their penultimate platinum regimen. Prior bevacizumab therapy was reported for 17% of those treated with Lynparza and 20% of those receiving placebo. Approximately 44% of patients on the Lynparza arm and 37% on placebo had received three or more lines of platinum-based treatment. All (100%) patients enrolled had gBRCA mutations.

All patients had a deleterious or suspected deleterious germline BRCA mutation as detected either by a local test (n=236) or central Myriad CLIA test (n=59), subsequently confirmed by BRACAnalysis CDx® (n=286).

SOLO-2 demonstrated a statistically significant improvement in investigator-assessed PFS in patients randomized to Lynparza as compared with placebo. Results from a blinded independent review were consistent. The final analysis of OS did not reach statistical significance. Efficacy results are presented in Table 20 and Figures 4 and 5.

Table 20 Efficacy Results - SOLO-2 (Investigator Assessment)
 | Lynparza tablets (n=196) | Placebo (n=99)
Progression-Free Survival
Number of events (%) | 107 (55%) | 80 (81%)
Median, months | 19.1 | 5.5
Hazard ratio [Hazard ratio from a Cox proportional hazards model including response to last platinum chemotherapy (complete response versus partial response) and time to disease progression in the penultimate platinum-based chemotherapy prior to enrollment (6-12 month versus >12 months) as covariates.] (95% CI) | 0.30 (0.22, 0.41)
p-value [The p-value is derived from a stratified log-rank test.] | <0.0001
Overall Survival
Number of events (%) | 116 (59) | 65 (66)
Median, months | 51.7 | 38.8
Hazard ratio (95% CI) | 0.74 (0.54, 1.00)
p-value | 0.0537

Figure 4 Kaplan-Meier Curves of Investigator-Assessed Progression-Free Survival – SOLO-2

Figure 5 Kaplan-Meier Curves of Overall Survival – SOLO-2

14.4 Adjuvant Treatment of Germline BRCA-mutated HER2-negative High Risk Early Breast Cancer

The efficacy of Lynparza was evaluated in OlympiA (NCT02032823), a randomized (1:1), double-blind, placebo-controlled, international study in patients with gBRCAm HER2-negative high risk early breast cancer who had completed definitive local treatment and neoadjuvant or adjuvant chemotherapy. Patients were randomized to receive Lynparza tablets 300 mg orally twice daily or placebo. Treatment was continued for up to 1 year, or until disease recurrence, or unacceptable toxicity. Patients were required to have completed at least 6 cycles of neoadjuvant or adjuvant chemotherapy containing anthracyclines, taxanes or both. Prior platinum for previous cancer (e.g., ovarian) or as adjuvant or neoadjuvant treatment for breast cancer was allowed. Patients with high-risk early breast cancer were defined as follows:

- patients who received prior neoadjuvant chemotherapy: patients with either triple negative breast cancer (TNBC) or hormone receptor positive breast cancer must have had residual invasive cancer in the breast and/or the resected lymph nodes (non-pathologic complete response) at the time of surgery. Additionally, patients with hormone receptor positive breast cancer must have had a score of ≥3 based on pre-treatment clinical and post-treatment pathologic stage (CPS), estrogen receptor (ER) status, and histologic grade as shown in Table 21.

Table 21 Early Breast Cancer Stage, Receptor Status, and Grade Scoring Requirements for Study Enrollment [Total score of ≥3 required for patients with hormone receptor positive breast cancer.]
Stage/feature |  | Points
Clinical Stage; (pre-treatment) | I/IIA | 0
Clinical Stage; (pre-treatment) | IIB/IIIA | 1
Clinical Stage; (pre-treatment) | IIIB/IIIC | 2
Pathologic Stage (post-treatment) | 0/I | 0
Pathologic Stage (post-treatment) | IIA/IIB/IIIA/IIIB | 1
Pathologic Stage (post-treatment) | IIIC | 2
Receptor status | ER positive | 0
Receptor status | ER negative | 1
Nuclear grade | Nuclear grade 1-2 | 0
Nuclear grade | Nuclear grade 3 | 1

- patients who received prior adjuvant chemotherapy: patients with TNBC must have had node positive disease or node negative disease with a ≥2cm primary tumor; patients with hormone receptor positive, HER2-negative breast cancer must have had ≥4 pathologically confirmed positive lymph nodes.

Randomization was stratified by hormone receptor status (hormone receptor positive versus triple negative), by prior neoadjuvant versus adjuvant chemotherapy, and by prior platinum use for breast cancer (yes versus no).

The major efficacy outcome measure was invasive disease free survival (IDFS), defined as the time from randomization to date of first recurrence, where recurrence is defined as invasive loco-regional, distant recurrence, contralateral invasive breast cancer, new cancer or death from any cause. An additional efficacy outcome measure was OS.

A total of 1836 patients were randomized, 921 to Lynparza and 915 to placebo. Demographic and baseline characteristics were well balanced between arms. The median age was 42 years. Sixty-seven percent (67%) of patients were White, 29% were Asian, and 3% were Black. Three percent (3%) of patients were Hispanic or Latino. Two patients (0.2%) in the Lynparza arm and four patients (0.4%) in the placebo arm were male. Sixty-one percent (61%) of patients were pre-menopausal. Eighty-nine percent (89%) of patients were ECOG performance status 0 and 11% ECOG PS 1. Eighty-two percent (82%) of patients had TNBC and 18% had hormone receptor-positive disease. Fifty percent (50%) of patients had received prior neoadjuvant and 50% received prior adjuvant chemotherapy. Ninety-four percent (94%) of patients received anthracycline and taxane chemotherapy. Twenty-six (26%) of patients overall had received prior platinum for breast cancer. Ninety percent (90%) of patients with hormone receptor positive breast cancer received concurrent endocrine therapy.

Patients enrolled based on local gBRCA test results provided a sample for retrospective confirmatory central testing with BRACAnalysis®. Out of 1836 patients enrolled into OlympiA, 1623 were confirmed as gBRCAm by Myriad BRACAnalysis®, either prospectively or retrospectively.

A statistically significant improvement in IDFS and OS was demonstrated in patients in the Lynparza arm compared with the placebo arm. Efficacy data for OlympiA (FAS) are presented in Table 22 and Figures 6 and 7.

Table 22 Efficacy Results – OlympiA
 | Lynparza tablets; (N=921) | Placebo; (N=915)
Invasive Disease Free Survival (IDFS) [Data from the pre-specified interim analysis (86% of the number of events for the planned final analysis).]
Number of events (%) | 106 (12) | 178 (20)
Hazard ratio (95% CI) [Based on the stratified Cox's Proportional Hazards Model.] | 0.58 (0.46, 0.74)
p‑value (2‑sided) [p-value from a stratified log-rank test. Compared with the allocated alpha of 0.005 for IDFS and 0.015 for OS.] | < 0.0001
3-year event-free rate, % (95% CI) [Percentage are calculated using Kaplan-Meier estimates.] | 86 (82.8, 88.4) | 77 (73.7, 80.1)
Overall Survival [Data from the pre-specified second interim analysis of OS (at ~330 IDFS events).]
Number of events (%) | 75 (8) | 109 (12)
Hazard ratio (95% CI) | 0.68 (0.50, 0.91)
p‑value (2-sided) | 0.0091
3-year event-free rate, % (95% CI) | 93 (90.8, 94.4) | 89 (86.7, 91)
CI = confidence interval.

Figure 6 Kaplan-Meier Curves of IDFS – OlympiA

Figure 7 Kaplan-Meier Curves of OS – OlympiA

14.5 Treatment of Germline BRCA-mutated HER2-negative Metastatic Breast Cancer

The efficacy of Lynparza was evaluated in OlympiAD (NCT02000622), an open-label randomized (2:1) study in patients with gBRCAm HER2-negative metastatic breast cancer. Patients were required to have received treatment with an anthracycline (unless contraindicated) and a taxane, in the neoadjuvant, adjuvant or metastatic setting. Patients with hormone receptor-positive disease must have progressed on at least 1 endocrine therapy (adjuvant or metastatic), or have disease that the treating healthcare provider believed to be inappropriate for endocrine therapy. Patients with prior platinum therapy were required to have no evidence of disease progress during platinum treatment. No prior treatment with a PARP inhibitor was permitted. Patients were randomized to Lynparza tablets 300 mg orally twice daily or healthcare provider’s choice of chemotherapy (capecitabine, eribulin, or vinorelbine, at standard doses) until progression or unacceptable toxicity. Randomization was stratified by prior use of chemotherapy for metastatic disease (yes vs no), hormone receptor status (hormone receptor positive vs triple negative), and previous use of platinum-based chemotherapy (yes vs no). The major efficacy outcome measure was PFS assessed by blinded independent central review (BICR) using RECIST version 1.1.

A total of 302 patients were randomized, 205 to Lynparza and 97 to chemotherapy. Among the 205 patients treated with Lynparza, the median age was 44 years (range: 22 to 76), 65% were White, 4% were males and all the patients had an ECOG PS of 0 or 1. Approximately 50% of patients had triple-negative tumors and 50% had estrogen receptor and/or progesterone receptor positive tumors and the proportions were balanced across treatment arms. Patients in each treatment arm had received a median of 1 prior chemotherapy regimen for metastatic disease; approximately 30% had not received a prior chemotherapy regimen for metastatic breast cancer. Twenty-one percent of patients in the Lynparza arm and 14% in the chemotherapy arm had received platinum therapy for metastatic disease. Seven percent of patients in each treatment arm had received platinum therapy for localized disease.

Of the 302 patients randomized onto OlympiAD, 299 were tested with the BRACAnalysis CDx® and 297 were confirmed to have deleterious or suspected deleterious gBRCAm status; 202 were randomized to the Lynparza arm and 95 to the healthcare provider’s choice of chemotherapy arm.

A statistically significant improvement in PFS was demonstrated for the Lynparza arm compared to the chemotherapy arm. Efficacy data for OlympiAD are displayed in Table 23 and Figure 8. Consistent results were observed across patient subgroups defined by study stratification factors. An exploratory analysis of investigator-assessed PFS was consistent with the BICR-assessed PFS results.

Table 23 Efficacy Results - OlympiAD (BICR-assessed)
 | Lynparza tablets; (n=205) | Chemotherapy; (n=97)
Progression-Free Survival
Number of events (%) | 163 (80%) | 71 (73%)
Median, months | 7.0 | 4.2
Hazard ratio (95% CI) [Hazard ratio is derived from a stratified log-rank test, stratified by ER, PgR negative versus ER and or PgR positive and prior chemotherapy (yes versus no).] | 0.58 (0.43, 0.80)
p-value [For PFS, p-value (2-sided) was compared to 0.05.] | 0.0009
Patients with Measurable Disease | n=167 | n=66
Objective Response Rate (95% CI) [Response based on confirmed responses. The confirmed complete response rate was 7.8% for Lynparza compared to 1.5% for chemotherapy arm.] | 52% (44, 60) | 23% (13, 35)
Overall Survival
Number of events (%) | 130 (63%) | 62 (64%)
Median, months | 19.3 | 17.1
Hazard ratio (95% CI) | 0.90 (0.66, 1.23)

Figure 8 Kaplan-Meier Curves of Progression-Free Survival - OlympiAD

14.6 First-Line Maintenance Treatment of Germline BRCA-mutated Metastatic Pancreatic Adenocarcinoma

The efficacy of Lynparza was evaluated in POLO (NCT02184195), a randomized (3:2), double-blind placebo-controlled, multi-center trial. Patients were required to have metastatic pancreatic adenocarcinoma with a deleterious or suspected deleterious germline BRCA mutation (gBRCAm) and absence of disease progression after receipt of first-line platinum-based chemotherapy for at least 16 weeks. Patients were randomized to receive Lynparza tablets 300 mg orally twice daily or placebo until disease progression or unacceptable toxicity. The major efficacy outcome measure was PFS by BICR using RECIST, version 1.1 modified to assess patients with clinical complete response at entry who were assessed as having no evidence of disease unless they had progressed based on the appearance of new lesions. Additional efficacy outcome measures were OS and ORR.

A total of 154 patients were randomized, 92 to Lynparza and 62 to placebo. The median age was 57 years (range 36 to 84); 54% were male; 92% were White, 4% were Asian, and 3% were Black; baseline ECOG PS was 0 (67%) or 1 (31%). The median time from initiation of first-line platinum-based chemotherapy to randomization was 5.8 months (range 3.4 to 33.4 months). Seventy-five percent (75%) of patients received FOLFIRINOX with a median of 9 cycles (range 4-61), 8% received FOLFOX or XELOX, 4% received GEMOX, and 3% received gemcitabine plus cisplatin; 49% achieved a complete or partial response to platinum-based chemotherapy.

All patients had a deleterious or suspected deleterious germline BRCA-mutation as detected by the Myriad BRACAnalysis® or BRACAnalysis CDx® at a central laboratory only (n=106), local BRCA test only (n=4), or both local and central testing (n=44). Among the 150 patients with central test results, 30% had a mutation in BRCA1; 69% had a mutation in BRCA2; and 1 patient (1%) had mutations in both BRCA1 and BRCA2.

POLO demonstrated a statistically significant improvement in BICR-assessed PFS in patients randomized to Lynparza as compared with placebo. The final analysis of OS did not reach statistical significance. Efficacy results of POLO are provided in Table 24 and Figure 9.

Table 24 Efficacy Results - POLO (BICR-assessed)
 | Lynparza tablets; (n=92) | Placebo; (n=62)
Progression-Free Survival
Number of events (%) [Number of events: Progression - Lynparza 55, placebo 44; death before BICR-documented progression - Lynparza 5, placebo 0.] | 60 (65) | 44 (71)
Median, months (95% CI) | 7.4 (4.1, 11.0) | 3.8 (3.5, 4.9)
Hazard ratio [Hazard ratio, 95% CI, and p-value calculated from a log-rank test. A hazard ratio <1 favors Lynparza.] (95% CI) | 0.53 (0.35, 0.81)
p-value | 0.0035
Overall Survival
Number of events (%) | 61 (66) | 47 (76)
Median, months (95% CI) | 19.0 (15.3, 26.3) | 19.2 (14.3, 26.1)
Hazard ratio† (95% CI) | 0.83 (0.56, 1.22)
p-value | 0.3487
Patients with Measurable Disease | n=78 | n=52
Objective Response Rate (95% CI) | 23% (14, 34) | 12% (4, 23)
Complete response (%) | 2 (2.6) | 0
Partial response (%) | 16 (21) | 6 (12)
Duration of Response (DOR)
Median time in months (95% CI) | 25 (15, NC) | 4 (2, NC)
NC Not calculable.

Figure 9 Kaplan-Meier Curves of BICR-Assessed Progression-Free Survival – POLO

14.7 HRR Gene-mutated Metastatic Castration-Resistant Prostate Cancer

The efficacy of Lynparza was evaluated in PROfound (NCT02987543), randomized, open-label, multi-center trial that evaluated the efficacy of Lynparza 300 mg twice daily versus a comparator arm of investigator’s choice of enzalutamide or abiraterone acetate in men with metastatic castration-resistant prostate cancer (mCRPC). All patients received a GnRH analog or had prior bilateral orchiectomy. Patients needed to have progressed on prior enzalutamide or abiraterone for the treatment of metastatic prostate cancer and/or CRPC and have a tumor mutation in one of 15 genes involved in the homologous recombination repair (HRR) pathway.

Patients were divided into two cohorts based on HRR gene mutation status. Patients with mutations in either BRCA1, BRCA2, or ATM were randomized in Cohort A; patients with mutations among 12 other genes involved in the HRR pathway (BARD1, BRIP1, CDK12, CHEK1, CHEK2, FANCL, PALB2, PPP2R2A, RAD51B, RAD51C, RAD51D, or RAD54L) were randomized in Cohort B; patients with co-mutations (BRCA1, BRCA2, or ATM plus a Cohort B gene) were assigned to Cohort A. Although patients with PPP2R2A gene mutations were enrolled in the trial, Lynparza is not indicated for the treatment of patients with this gene mutation due to unfavorable risk-benefit. Patients were randomized (2:1), 256 to Lynparza arm and 131 to enzalutamide or abiraterone acetate arm; in Cohort A there were 245 (162 Lynparza arm and 83 in enzalutamide or abiraterone acetate arm) and in Cohort B there were 142 patients (94 in Lynparza arm and 48 in enzalutamide or abiraterone acetate arm). Randomization was stratified by prior receipt of taxane chemotherapy and presence of measurable disease by RECIST 1.1. Treatment was continued until objective radiological disease progression determined by BICR. Upon radiological progression confirmed by BICR, patients randomized to enzalutamide or abiraterone acetate were given the option to switch to Lynparza. Patients with HRR gene mutations were identified by tissue-based testing using the Foundation Medicine FoundationOne® clinical trial HRR assay performed at a central laboratory.

Determination of deleterious or suspected deleterious somatic or germline HRR mutation status in line with the FDA-approved mutation classification and testing criteria for the Foundation Medicine F1CDx tissue-based assay and assessment of the germline-BRCA status using the Myriad BRACAnalysis CDx blood-based assay was performed retrospectively. Representation of individual gene mutations by cohort is provided in Table 25. No patients were enrolled who had mutations in two of the 15 pre-specified HRR genes: FANCL and RAD51C.

Table 25 Frequency of Patients with HRR Mutations Enrolled in PROfound
HRR Mutation | Cohort A; N=245; n (%) | Cohort B [Three patients with single BRCA2 or ATM gene mutations and 1 patient with co-occurring BRCA2+CDK12 gene mutations were incorrectly assigned to Cohort B.]; N=142; n (%)
Single mutation | 224 (91) | 135 (95)
BRCA2 | 127 (52) | 1 (<1)
ATM | 84 (34) | 2 (1)
BRCA1 | 13 (5) | 0
CDK12 | 0 | 89 (63)
CHEK2 | 0 | 12 (8)
PPP2R2A [Lynparza is not indicated for patients with PPP2R2A mutations.] | 0 | 10 (7)
RAD51B | 0 | 5 (4)
RAD54L | 0 | 5 (4)
PALB2 | 0 | 4 (3)
BRIP1 | 0 | 3 (2)
CHEK1 | 0 | 2 (1)
BARD1 | 0 | 1 (<1)
RAD51D | 0 | 1 (<1)
Co-occurring mutation [Patients with co-occurring mutations (BRCA1, BRCA2, or ATM plus a Cohort B gene) were assigned to Cohort A.] | 21 (9) | 7 (5)

In Cohort A+B, the median age was 69 years (range: 47 to 91 years) in both arms; 69% were White, 29% were Asian, and 1% were Black. The ECOG performance score was 0 or 1 in most patients (95%) in both arms. In patients treated with Lynparza, the proportion of patients with RECIST 1.1 measurable disease at baseline was 58%, including 17% with lung and 10% with liver metastases, respectively. At randomization, 66% of patients had received prior taxane chemotherapy, 40% had received enzalutamide, 38% had received abiraterone acetate, and 20% had received both enzalutamide and abiraterone acetate. Patient characteristics were well-balanced between arms.

The major efficacy outcome of the study was radiological progression-free survival (rPFS) (Cohort A) as determined by BICR using RECIST version 1.1 and Prostate Cancer Clinical Trials Working Group 3 (PCWG3) (bone) criteria. Additional efficacy outcomes included confirmed objective response rate (ORR) (Cohort A), rPFS (combined Cohorts A+B) as assessed by BICR, and overall survival (OS) (Cohort A).

PROfound demonstrated a statistically significant improvement in BICR-assessed rPFS for Lynparza compared to investigator’s choice of enzalutamide or abiraterone acetate in Cohort A and Cohort A+B. In an exploratory analysis for patients in Cohort B, the median rPFS was 4.8 months for Lynparza vs 3.3 months for comparator with a HR of 0.88 (95% CI 0.58, 1.36). The major efficacy outcome was supported by a statistically significant improvement in ORR by BICR for patients with measurable disease at baseline in Cohort A. In Cohort B, ORR by BICR was 3.7% (95% CI 0.5, 12.7) in Lynparza treated patients and 8.3% (95% CI 1.0, 27.0) in patients treated with enzalutamide or abiraterone acetate.

The final analysis of overall survival (OS) demonstrated a statistically significant improvement in OS in patients randomized to Lynparza compared to patients in the enzalutamide or abiraterone acetate arm in Cohort A.

Efficacy results of PROfound are provided in Tables 26 and 27 and Figures 10 and 11.

Table 26 Efficacy Results - PROfound (BICR-assessed)
 | Cohort A |  | Cohort A+B [Although 10 patients with PPP2R2A mutation were included in all analyses of Cohort A+B, Lynparza is not indicated for this population due to unfavorable risk-benefit.]
 | Lynparza tablets (n=162) | Enzalutamide or Abiraterone acetate (n=83) | Lynparza tablets (n=256) | Enzalutamide or Abiraterone acetate (n=131)
Radiological Progression-Free Survival (rPFS)
Number of events (%) | 106 (65) | 68 (82) | 180 (70) | 99 (76)
Median (95% CI), in months | 7.4 (6.2, 9.3) | 3.6 (1.9, 3.7) | 5.8 (5.5, 7.4) | 3.5 (2.2, 3.7)
Hazard ratio (95% CI) [The HR and CI were calculated using a Cox proportional hazards model adjusted for prior taxane use and measurable disease. An HR <1 favors Lynparza 300 mg taken orally twice daily.] | 0.34 (0.25, 0.47) |  | 0.49 (0.38, 0.63)
p-value [The analysis was performed using the log-rank test stratified by prior taxane use and measurable disease.] | <0.0001 |  | <0.0001
Confirmed ORR
Patients with measurable disease at baseline | n=84 | n=43 | - | -
ORR, n (%) | 28 (33) | 1 (2) | - | -
(95% CI) | (23, 45) | (0, 12) | - | -
p-value | <0.0001 |  | -
Overall Survival | n=162 | n=83 | - | -
Number of events (%) | 91 (56) | 57 (69) | - | -
Median (95% CI), in months | 19.1 (17.4, 23.4) | 14.7 (11.9, 18.8) | - | -
Hazard ratio (95% CI) | 0.69 (0.50, 0.97) |  | -
p-value | 0.0175 |  | -
CI Confidence interval

Figure 10 Kaplan-Meier Curves of BICR-Assessed rPFS – PROfound – Cohort A

Consistent results were observed in exploratory analyses of rPFS for patients who received or did not receive prior taxane therapy and for those with germline-BRCA mutations identified using the Myriad BRACAnalysis CDx assay compared with those with BRCA mutations identified using the Foundation Medicine F1CDx assay.

Figure 11 Kaplan-Meier Curves of Overall Survival – PROfound – Cohort A

Response data by HRR mutations for patients in the Lynparza arm are presented in Table 27. In the comparator arm of Cohorts A and B, a total of three patients achieved a partial response, including one patient with an ATM mutation alone and 2 patients with co-occurring mutations (one with PALB2+PPP2R2A and one with CDK12+PALB2).

Table 27 Response Rate and Duration of Response by HRR Mutation in Patients with Measurable Disease at Baseline on the Lynparza Arm – PROfound (BICR-assessed)
HRR mutation [No patients with FANCL or RAD51C enrolled. Three patients with PPP2R2A mutations had measurable disease, however, Lynparza is not indicated for patients with PPP2R2A mutation.] | Patients; (N=138) | Confirmed ORR [In patients with a single BRCA2 mutation the median duration of response in the Lynparza arm (n=24) was 5.6 months (95% C.I: 5.5, 9.2). In the 3 responders with a single ATM mutation in the Lynparza arm, the duration of response ranged from 5.8+ to 9.0 months. In the 2 responders with a single CDK12 mutation in the Lynparza arm, the duration of response was 3.7 and 7.2 months. + denotes ongoing response.]
HRR mutation [No patients with FANCL or RAD51C enrolled. Three patients with PPP2R2A mutations had measurable disease, however, Lynparza is not indicated for patients with PPP2R2A mutation.] | Patients; (N=138) | n (%) | 95% CI
Single mutation
BRCA2 | 43 | 24 (56) | (40, 71)
ATM | 30 | 3 (10) | (2, 27)
CDK12 | 34 | 2 (6) | (1, 20)
BRCA1 | 6 | SD, PD (4), NE | NA
CHEK2 | 4 | SD (2), PD (2) | NA
BRIP1 | 2 | SD, PD | NA
PALB2 | 2 | SD, PD | NA
CHEK1 | 1 | PD | NA
RAD51B | 1 | SD | NA
RAD51D | 1 | PD | NA
RAD54L | 1 | SD | NA
Co-occurring mutations
BRCA2/CDK12 | 2 | PR, SD | NA
BRCA2/ATM | 2 | SD, SD | NA
BRCA2/BARD1 | 1 | PD | NA
BRCA2/CHEK2 | 1 | SD | NA
CDK12/CHEK1 | 1 | SD | NA
CDK12/PALB2 | 1 | PD | NA
BRCA2/CDK12/CHEK2 | 1 | PD | NA
BRCA2/CHEK2/RAD51D | 1 | SD | NA
PR Partial response; SD Stable disease; PD Progressive disease; NE Not evaluable; NA Not applicable due to small numbers or lack of response.

14.8 Treatment of BRCA-mutated Metastatic Castration-Resistant Prostate Cancer in Combination with Abiraterone and Prednisone or Prednisolone

The efficacy of Lynparza in the treatment of patients with mCRPC was investigated in PROpel (NCT03732820), a randomized, double-blind, placebo-controlled, multi-center study that compared the efficacy of Lynparza in combination with abiraterone with placebo plus abiraterone for patients with mCRPC. Patients (n=796) were randomized (1:1) to receive Lynparza tablets 300 mg orally twice daily in combination with abiraterone 1000 mg daily (n=399) compared with placebo plus abiraterone (n=397). All patients received either prednisone or prednisolone 5 mg twice daily, and a GnRH analog or prior bilateral orchiectomy. Patients with prior treatment with abiraterone were excluded. Prior docetaxel for localized or metastatic hormone-sensitive prostate cancer (mHSPC) was allowed. Randomization was stratified by metastases (bone only, visceral, or other) and docetaxel treatment at mHSPC stage (yes or no). Lynparza treatment was continued until objective radiological disease progression determined by investigator or unacceptable toxicity.

BRCA gene mutation (BRCAm) status was assessed after randomization and before primary analysis by both NGS-based tumor tissue and ctDNA tests. BRCAm classification criteria in line with the FDA approved assays were used to determine the deleterious and suspected deleterious somatic or germline mutation status of patients.

The major efficacy outcome measure was investigator-assessed rPFS evaluated according to RECIST, version 1.1 and Prostate Cancer Working Group (PCWG3) (bone) criteria. Overall survival (OS) was an additional efficacy outcome measure.

Of the 796 patients tested, 85 (11%) had BRCAm determined by either a positive ctDNA test (9%) or a tumor tissue test (6%). Among these 85 patients, the median age was 68 years (range 43 to 85), and 67% were 65 years or older; 72% were White, 22% Asian, and 2% Black or African American; 66% had ECOG performance status (PS) 0 and 34% had ECOG PS 1; 25% had prior docetaxel treatment for mHSPC; 53% had bone-only metastases, 15% had visceral metastases, and 32% had other metastases.

A statistically significant improvement in rPFS for Lynparza/abiraterone compared to placebo/abiraterone was observed in the intention to treat (ITT) population. In an exploratory analysis in the subgroup of 711 patients without an identified BRCAm, the rPFS hazard ratio was 0.77 (95% CI: 0.63, 0.96) and the OS hazard ratio was 0.92 (95% CI: 0.74, 1.14), indicating that the improvement in the ITT population was primarily attributed to the results seen in the subgroup of patients with BRCAm.

Results of an exploratory analysis in the subgroup of 85 patients on PROpel with BRCAm are summarized in Table 28 and Figure 12 and 13.

Results from the BICR assessment were consistent with the investigator-assessed rPFS results.

Table 28 Efficacy Results – PROpel (Patients with BRCAm)
 | Lynparza/abiraterone; N = 47 | Placebo/abiraterone; N = 38
Radiological Progression-Free Survival (rPFS) [Investigator-assessed.]
Events, n (%) | 14 (30) | 28 (74)
Median (95% CI), months | NR (NR, NR) | 8 (6, 15)
Hazard ratio (95% CI) [Calculated using an unstratified univariable Cox proportional hazards model.] | 0.24 (0.12, 0.45)
Overall Survival (OS)
Events, n (%) | 13 (28) | 25 (66)
Median (95% CI), months | NR (NR, NR) | 23 (18, 34)
Hazard ratio (95% CI) | 0.30 (0.15, 0.59)
NR: Not reached.

Figure 12 Kaplan-Meier Curves of rPFS – PROpel (Patients with BRCAm, Investigator Assessment)

Figure 13 Kaplan-Meier Curves of OS – PROpel (Patients with BRCAm)

16 HOW SUPPLIED/STORAGE AND HANDLING

Lynparza is available as 150 mg and 100 mg tablets.

- 150 mg tablets: green to green/grey, oval, bi-convex, film-coated tablet, with debossment ‘OP150’ on one side and plain on the reverse, are available in:
  ∘ Bottles of 60 tablets (NDC 0310-0679-60) and
  ∘ Bottles of 120 tablets (NDC 0310-0679-12).
- 100 mg tablets: yellow to dark yellow, oval, bi-convex, film-coated tablet, with debossment ‘OP100’ on one side and plain on the reverse, are available in:
  ∘ Bottles of 60 tablets (NDC 0310-0668-60) and
  ∘ Bottles of 120 tablets (NDC 0310-0668-12).

Store at 20ºC to 25ºC (68ºF to 77ºF), excursions permitted to 15ºC to 30ºC (59ºF to 86ºF) [see USP Controlled Room Temperature]. Store in original bottle to protect from moisture.

17 PATIENT COUNSELING INFORMATION

Advise the patient to read the FDA-approved patient labeling (Medication Guide).

MDS/AML

Advise patients to contact their healthcare provider if they experience weakness, feeling tired, fever, weight loss, frequent infections, bruising, bleeding easily, breathlessness, blood in urine or stool, and/or laboratory findings of low blood cell counts, or a need for blood transfusions. This may be a sign of hematological toxicity or a more serious uncommon bone marrow problem called ‘myelodysplastic syndrome’ (MDS) or ‘acute myeloid leukemia’ (AML) which have been reported in patients treated with Lynparza [see Warnings and Precautions (5.1)].

Pneumonitis

Advise patients to contact their healthcare provider if they experience any new or worsening respiratory symptoms including shortness of breath, fever, cough, or wheezing [see Warnings and Precautions (5.2)].

Venous Thromboembolism

Advise patients to immediately report any signs or symptoms of thromboembolism such as pain or swelling in an extremity, shortness of breath, chest pain, tachypnea, and tachycardia [see Warnings and Precautions (5.3)].

Hepatotoxicity, Including Drug-Induced Liver Injury

Inform patients that liver problems, including drug-induced liver injury and abnormalities in liver tests, may develop during Lynparza treatment. Advise patients to contact their healthcare provider immediately if they experience abdominal discomfort, dark urine, or jaundice [see Warnings and Precautions (5.4)].

Embryo-Fetal Toxicity

Inform pregnant women of the risk to a fetus and potential loss of the pregnancy. Advise females to inform their healthcare provider of known or suspected pregnancy [see Use in Specific Populations (8.1)].

Advise females of reproductive potential to use effective contraception during treatment with Lynparza and for 6 months after the last dose [see Use in Specific Populations (8.3)].

Advise male patients with female partners of reproductive potential or who are pregnant to use effective contraception during treatment and for 3 months after receiving the last dose of Lynparza. Advise male patients not to donate sperm during therapy and for 3 months following the last dose of Lynparza [see Warnings and Precautions (5.5) and Use in Specific Populations (8.3)].

Lactation

Advise patients not to breastfeed while taking Lynparza and for one month after receiving the last dose [see Use in Specific Populations (8.2)].

Drug Interactions

Advise patients and caregivers to inform their healthcare provider of all concomitant medications, including prescription medicines, over-the-counter drugs, vitamins, and herbal products. Inform patients to avoid grapefruit, grapefruit juice, Seville oranges, and Seville orange juice while taking Lynparza [see Drug Interactions (7.2)].

Nausea/Vomiting

Advise patients that mild or moderate nausea and/or vomiting is very common in patients receiving Lynparza and that they should contact their healthcare provider who will advise on available antiemetic treatment options [see Adverse Reactions (6.1)].

Distributed by:

AstraZeneca Pharmaceuticals LP

Wilmington, DE 19850

© AstraZeneca 2025

Medication Guide

Lynparza® (Lin-par-zah)

(olaparib)

tablets

What is the most important information I should know about Lynparza?

Lynparza may cause serious side effects, including:

- Bone marrow problems called Myelodysplastic Syndrome (MDS) or Acute Myeloid Leukemia (AML). Some people who have received previous treatment with chemotherapy, radiotherapy or certain other medicines for their cancer have developed MDS or AML during treatment with Lynparza. MDS or AML may lead to death.
  Symptoms of low blood cell counts are common during treatment with Lynparza, but can be a sign of serious bone marrow problems, including MDS or AML. Symptoms may include:

∘ weakness
∘ weight loss
∘ fever
∘ frequent infections

∘ blood in urine or stool
∘ shortness of breath
∘ feeling very tired
∘ bruising or bleeding more easily

Your healthcare provider will do blood tests to check your blood cell counts:

  ∘ before treatment with Lynparza
  ∘ every month during treatment with Lynparza
  ∘ weekly if you have low blood cell counts that last a long time.
- Lung problems (Pneumonitis). Lynparza can cause serious lung problems that can lead to death. Tell your healthcare provider if you have any new or worsening symptoms of lung problems, including shortness of breath, fever, cough, or wheezing. Your healthcare provider may do a chest x-ray if you have any of these symptoms.
- Blood clots (Venous Thromboembolism, [VTE]). Some people may develop a blood clot in a deep vein, usually in the leg (venous thrombosis), or a clot in the lungs (pulmonary embolism, [PE]) which may be severe or lead to death. Tell your healthcare provider right away if you have any symptoms such as pain or swelling in an extremity, shortness of breath, chest pain, breathing that is more rapid than normal (tachypnea), or heart beats faster than normal (tachycardia). Your healthcare provider will monitor you for these symptoms and may prescribe blood thinner medicine.
- Liver problems, including Drug-Induced Liver Injury (DILI). People taking Lynparza may develop liver problems which may be severe and can lead to death. Your healthcare provider should do blood tests before and during your treatment with Lynparza. Tell your healthcare provider right away if you notice discomfort on the right side of your stomach-area (abdominal), dark or “tea-colored” urine, or yellowing of your skin or the whites of your eyes (jaundice).

Your healthcare provide may change your dose, temporarily stop, or permanently stop treatment with Lynparza if you get certain side effects.

See “What are the possible side effects of LYNPARZA?” for more information about side effects.

What is Lynparza?

Lynparza is a prescription medicine used to treat adults who have:

- ovarian, fallopian tube, or primary peritoneal cancer:
  ∘ that is advanced and has a certain type of inherited (germline) or acquired (somatic) abnormal BRCA gene. Lynparza is used as maintenance treatment after the cancer has responded to your first treatment with platinum-based chemotherapy.
  ∘ in combination with another anti-cancer medicine called bevacizumab when your cancer is advanced and homologous recombination deficiency (HRD) positive, which is identified by a certain type of abnormal BRCA gene or a positive laboratory tumor test for genomic instability. Lynparza is used as maintenance treatment after the cancer has responded to your first treatment with platinum-based chemotherapy.
  ∘ that has come back and has a certain type of inherited or acquired abnormal BRCA gene. Lynparza is used as maintenance treatment after the cancer has responded to treatment with platinum-based chemotherapy.
- human epidermal growth factor receptor 2 (HER2)-negative breast cancer with a certain type of inherited abnormal BRCA gene:
  ∘ with a high risk of recurrence. Lynparza is given after surgery (treatment after surgery is called adjuvant therapy). You should have received chemotherapy medicines before or after surgery to remove the tumor.
  ∘ that has spread to other parts of the body (metastatic). You should have received chemotherapy medicines, either before or after your cancer has spread. If you have hormone receptor (HR)-positive breast cancer, you should have either already received hormonal therapy or hormonal therapy is not the right treatment for you.
- pancreatic cancer (adenocarcinoma) that has spread to other parts of the body and has a certain type of abnormal inherited BRCA gene. Lynparza is used as maintenance treatment after your cancer has not progressed on at least 16 weeks of your first treatment with platinum-based chemotherapy.
- metastatic castration-resistant prostate cancer (mCRPC):
  ∘ with a certain type of inherited or acquired abnormal homologous recombination repair (HRR) genes. Lynparza is used when the cancer has spread to other parts of the body and no longer responds to a medical or surgical treatment that lowers testosterone and has progressed after treatment with other anti-cancer medicines called enzalutamide or abiraterone.
  ∘ with a certain type of abnormal BRCA gene, and the cancer has spread to other parts of the body and no longer responds to a medical or surgical treatment that lowers testosterone. Lynparza is used in combination with another anti-cancer medicine, abiraterone, together with the steroid medicine prednisone or prednisolone.

Your healthcare provider will perform a test to make sure that Lynparza is right for you.

It is not known if Lynparza is safe and effective in children.

Before taking Lynparza, tell your healthcare provider about all of your medical conditions, including if you:

- have lung or breathing problems
- have kidney problems
- are pregnant, become pregnant, or plan to become pregnant. Lynparza can harm your unborn baby and may cause loss of pregnancy (miscarriage).
  Females who are able to become pregnant:
  ∘ Your healthcare provider may do a pregnancy test before you start treatment with Lynparza.
  ∘ You should use effective birth control (contraception) during treatment with Lynparza and for 6 months after the last dose of Lynparza. Talk to your healthcare provider about birth control methods that may be right for you.
  ∘ Tell your healthcare provider right away if you become pregnant or think you might be pregnant following treatment with Lynparza.
    Males with female partners who are pregnant or able to become pregnant:
  ∘ You should use effective contraception during treatment with Lynparza and for 3 months after the last dose of Lynparza.
  ∘ Do not donate sperm during treatment with Lynparza and for 3 months after your last dose.
- are breastfeeding or plan to breastfeed. It is not known if Lynparza passes into your breast milk. Do not breastfeed during treatment with Lynparza and for 1 month after receiving the last dose of Lynparza. Talk to your healthcare provider about the best way to feed your baby during this time.

Tell your healthcare provider about all the medicines you take, including prescription and over-the-counter medicines, vitamins, and herbal supplements. Taking Lynparza and certain other medicines may affect how Lynparza works and may cause side effects.

How should I take Lynparza?

- Take Lynparza tablets exactly as your healthcare provider tells you.
- Your healthcare provider will decide how long you stay on treatment.
- Do not change your dose or stop taking Lynparza unless your healthcare provider tells you to.
- Take Lynparza by mouth 2 times a day with or without food.
- Each dose should be taken about 12 hours apart.
- Swallow Lynparza tablets whole. Do not chew, crush, dissolve, or divide the tablets.
- If you are taking Lynparza for early breast cancer and you have HR‑positive disease, you should continue to take hormonal therapy during your treatment with Lynparza.
- If you are taking Lynparza for prostate cancer and you are receiving gonadotropin-releasing hormone (GnRH) analog therapy, you should continue with this treatment during your treatment with Lynparza unless you have had a surgery to remove both of your testicles (surgical castration) to lower the amount of testosterone in your body.
- If you miss a dose of Lynparza, take your next dose at your usual scheduled time. Do not take an extra dose to make up for a missed dose.
- If you take too much Lynparza, call your healthcare provider or go to the nearest hospital emergency room right away.

What should I avoid while taking Lynparza?

Avoid grapefruit, grapefruit juice, Seville oranges and Seville orange juice during treatment with Lynparza since they may increase the level of Lynparza in your blood.

What are the possible side effects of Lynparza?

Lynparza may cause serious side effects.

- See “What is the most important information I should know about Lynparza?”

The most common side effects of Lynparza when used alone are:

- tiredness or weakness
- low red blood cell counts
- diarrhea
- loss of appetite
- headache
- changes in the way food tastes

- cough
- low white blood cell counts
- shortness of breath
- dizziness
- indigestion or heartburn
- low platelet counts

The most common side effects of Lynparza when used in combination with bevacizumab are:

- tiredness or weakness
- low red blood cell counts
- diarrhea

- low white blood cell counts
- urinary tract infection
- headache

The most common side effects of Lynparza when used in combination with abiraterone and prednisone or prednisolone are:

- low red blood cell counts
- tiredness or weakness
- diarrhea
- loss of appetite

- low white blood cell counts
- dizziness
- stomach-area (abdominal) pain

Nausea or vomiting is common during treatment with Lynparza. Tell your healthcare provider if you get nausea or vomiting. Your healthcare provider may prescribe medicines to treat these symptoms.

These are not all of the possible side effects of Lynparza.

Call your healthcare provider for medical advice about side effects. You may report side effects to FDA at 1-800-FDA-1088.

How should I store Lynparza?

- Store Lynparza at room temperature, between 68°F to 77°F (20°C to 25°C).
- Store Lynparza in the original bottle to protect it from moisture.

Keep Lynparza and all medicines out of reach of children.

General information about the safe and effective use of Lynparza.

Medicines are sometimes prescribed for purposes other than those listed in a Medication Guide. Do not use Lynparza for a condition for which it was not prescribed. Do not give Lynparza to other people, even if they have the same symptoms that you have. It may harm them.

You can ask your pharmacist or healthcare provider for information about Lynparza that is written for health professionals.

What are the ingredients in Lynparza?

Active ingredient: olaparib

Inactive ingredients:

Tablet contains: copovidone, mannitol, colloidal silicon dioxide and sodium stearyl fumarate

Tablet coating contains: hypromellose, polyethylene glycol 400, titanium dioxide, ferric oxide yellow and ferrosoferric oxide (150 mg tablet only)

Lynparza is a registered trademark of the AstraZeneca group of companies.

© AstraZeneca 2025

Distributed by:

AstraZeneca Pharmaceuticals LP

Wilmington, DE 19850

For more information, call 1-800-236-9933 or go to www.Lynparza.com.

This Medication Guide has been approved by the U.S. Food and Drug Administration. Revised: 07/2025

PACKAGE/LABEL PRINCIPAL DISPLAY PANEL – 100 mg

NDC 0310-0668-60

Lynparza®

(olaparib) tablets

100 mg

Dispense accompanying

Medication Guide to each patient.

60 Tablets

Rx only

AstraZeneca

PACKAGE/LABEL PRINCIPAL DISPLAY PANEL – 150 mg

NDC 0310-0679-12

Lynparza®

(olaparib) tablets

150 mg

Dispense accompanying

Medication Guide to each patient.

120 Tablets

Rx only

AstraZeneca

Package/Label Display Panel

NDC 0310-0569-60

Lynparza

(olaparib) tablets

100 mg

Dispense accompanying

Medication Guide to each

Patient.

60 Tablets

Rx Only

AstraZeneca

Package/Label Display Panel

NDC 0310-0578-60

Lynparza

(olaparib) tablets

150 mg

Dispense accompanying

Medication Guide to each patient.

60 Tablets

Rx only

AstraZeneca